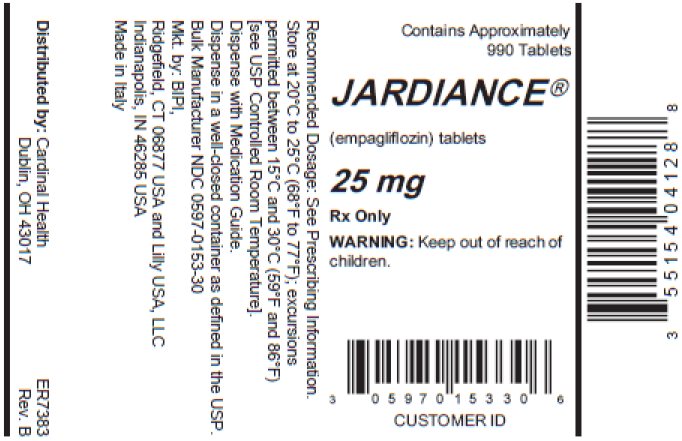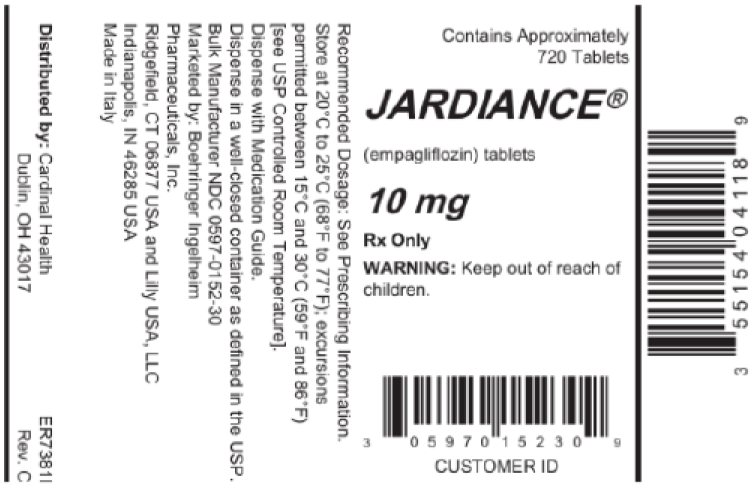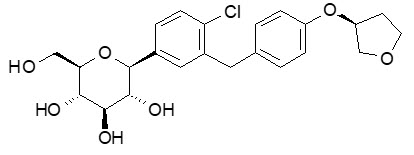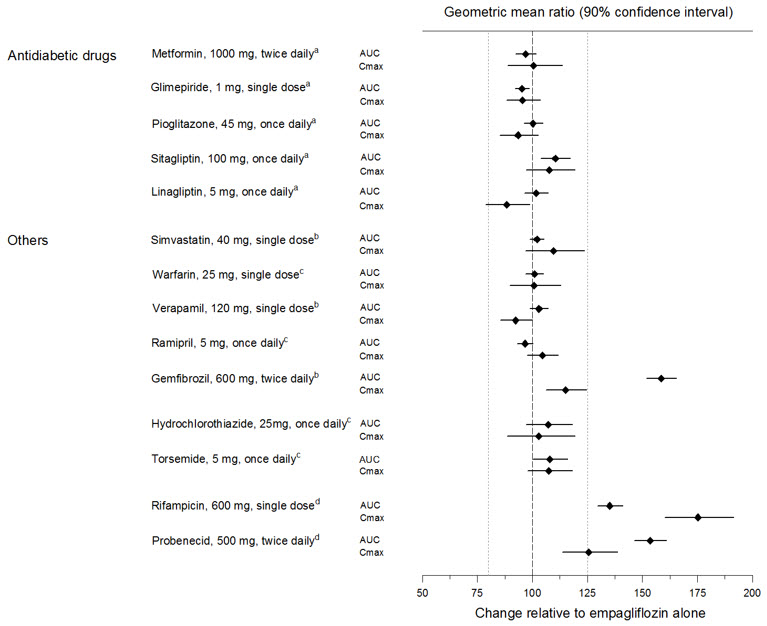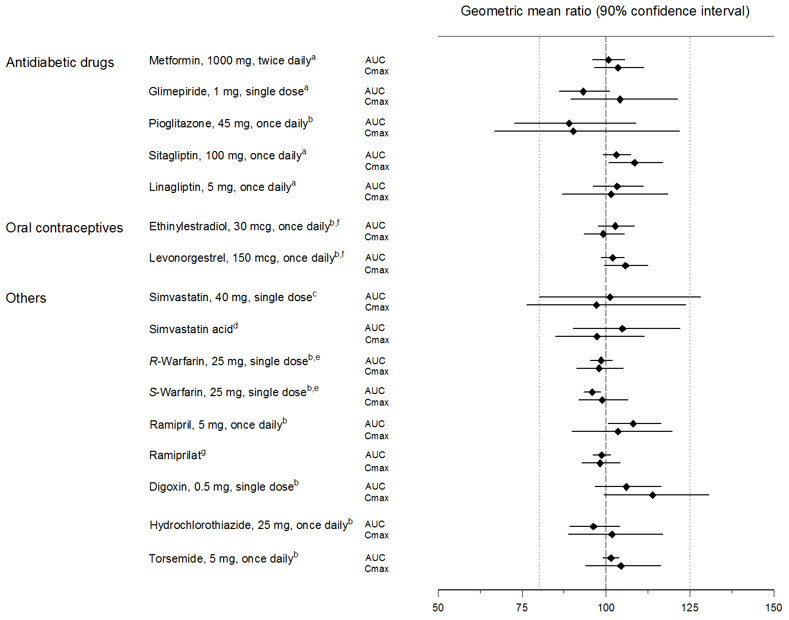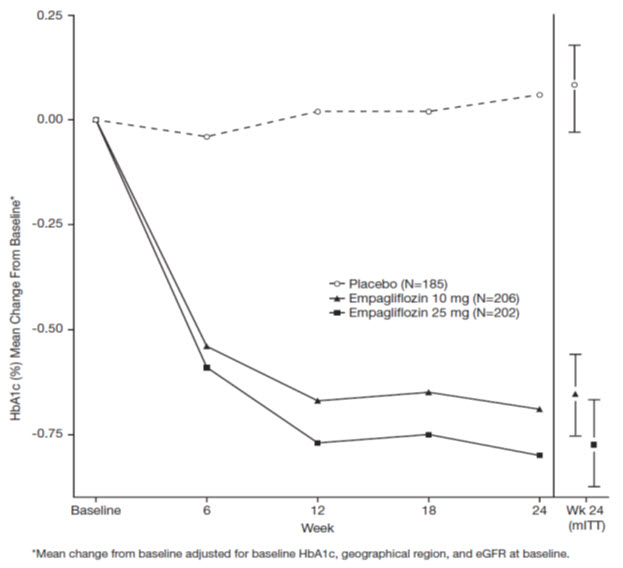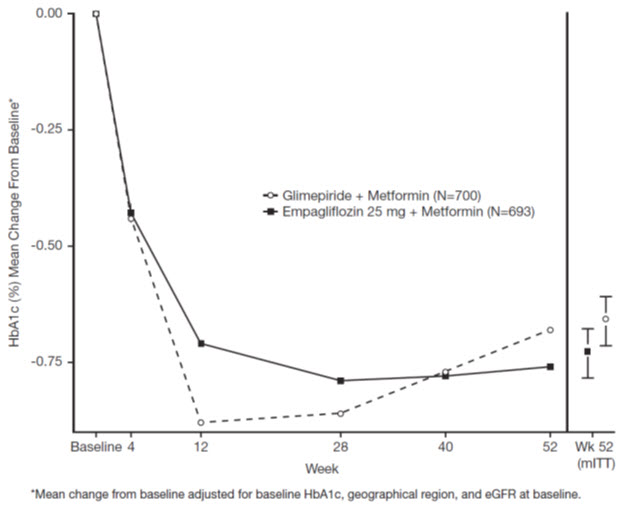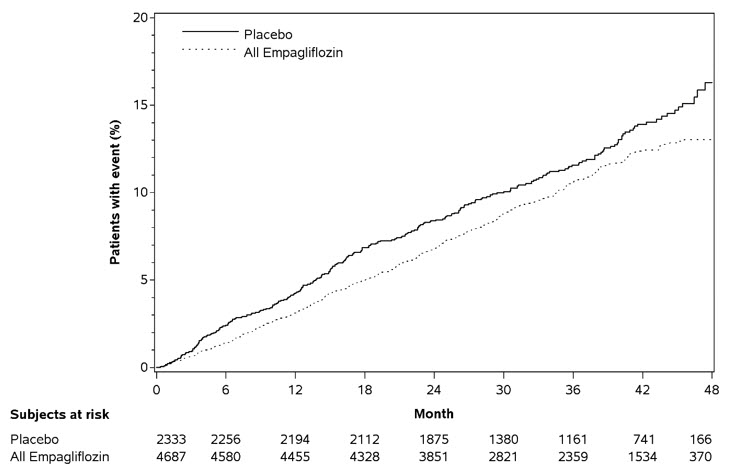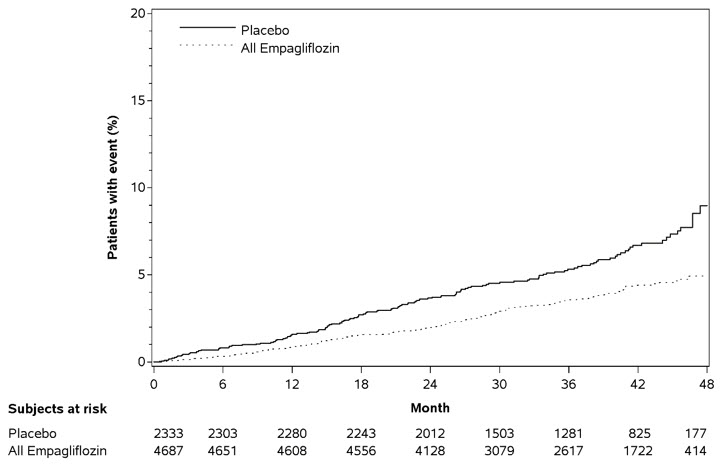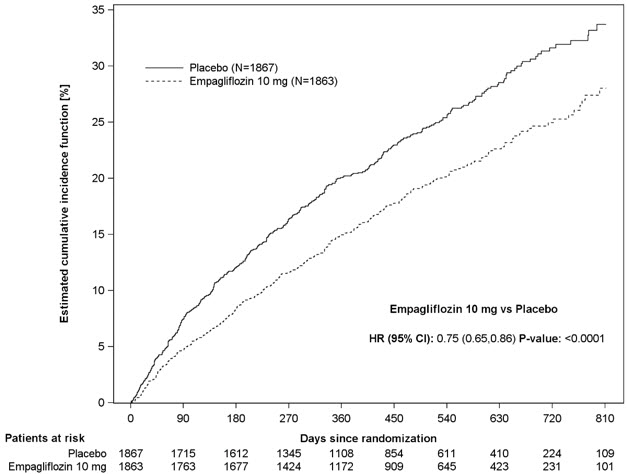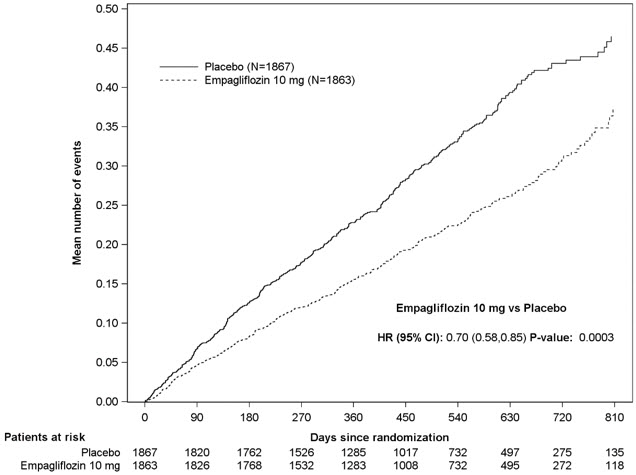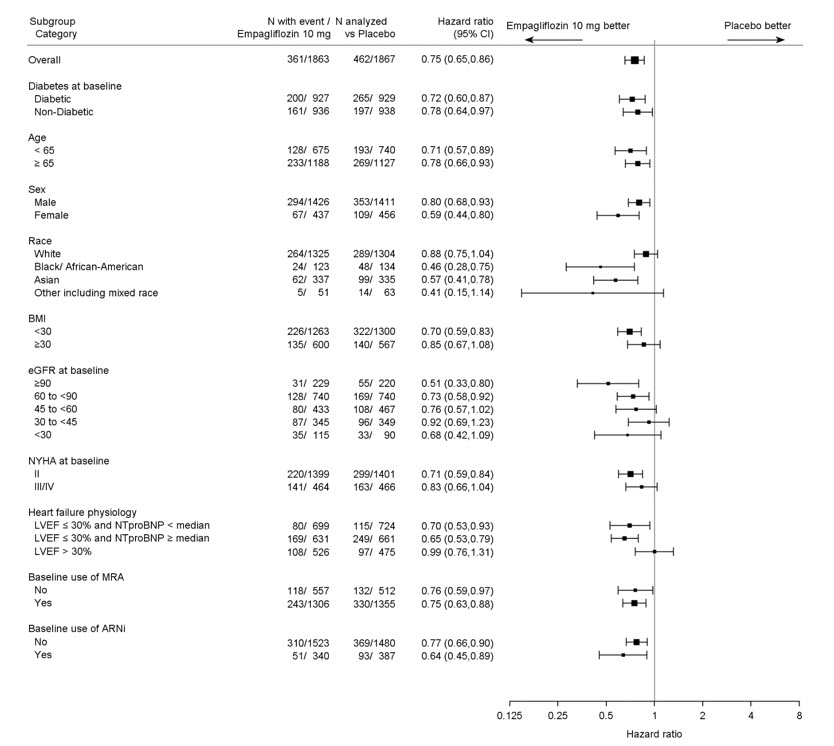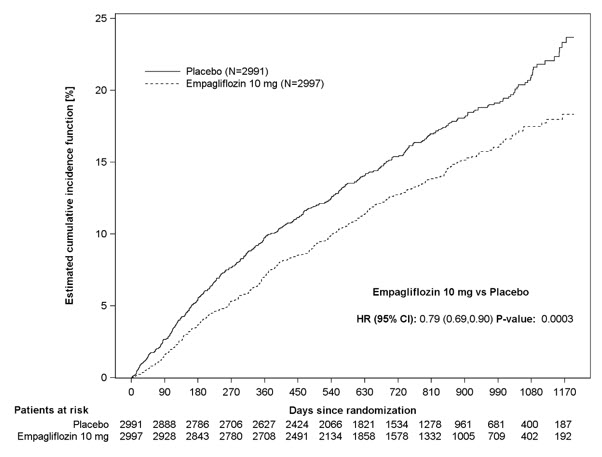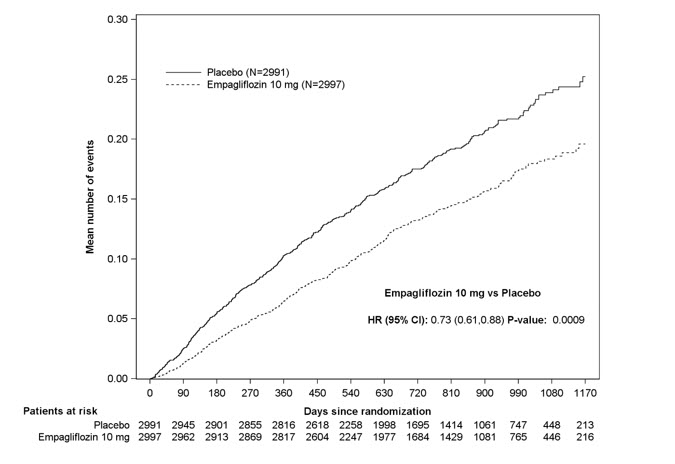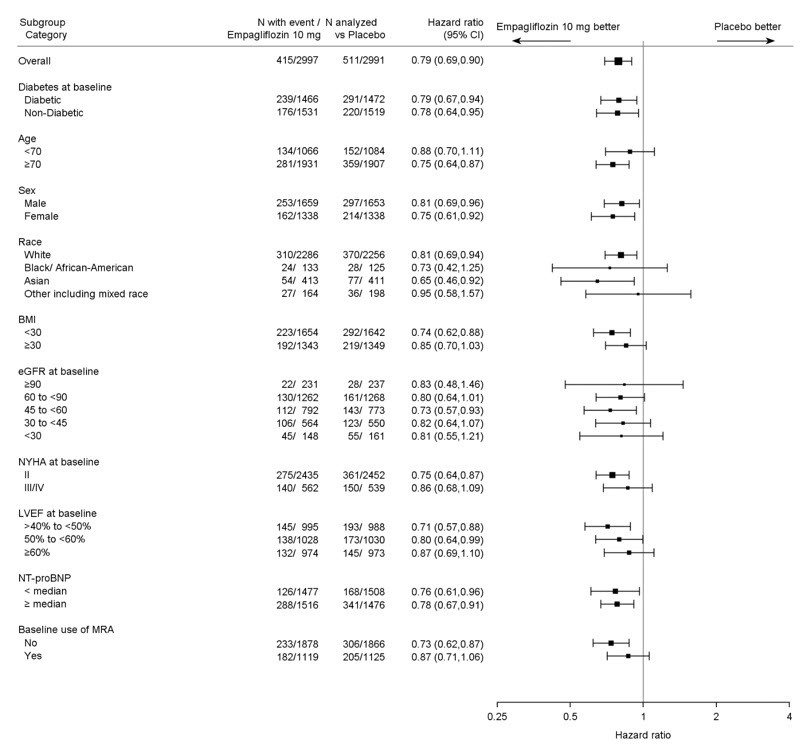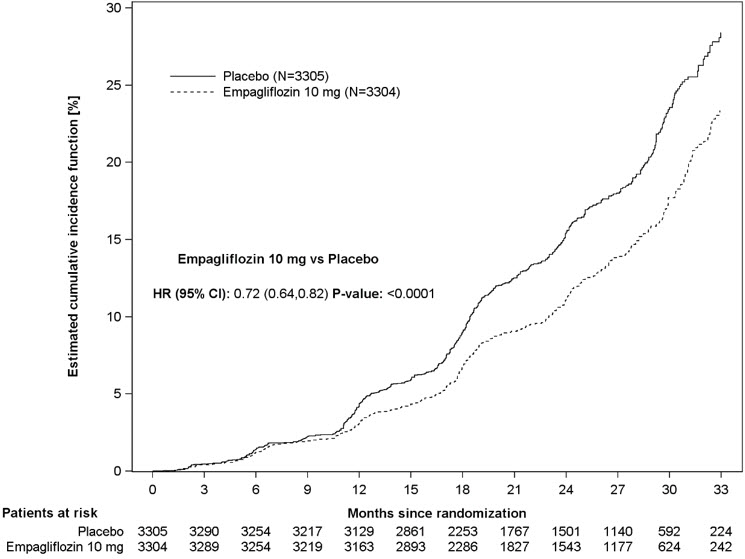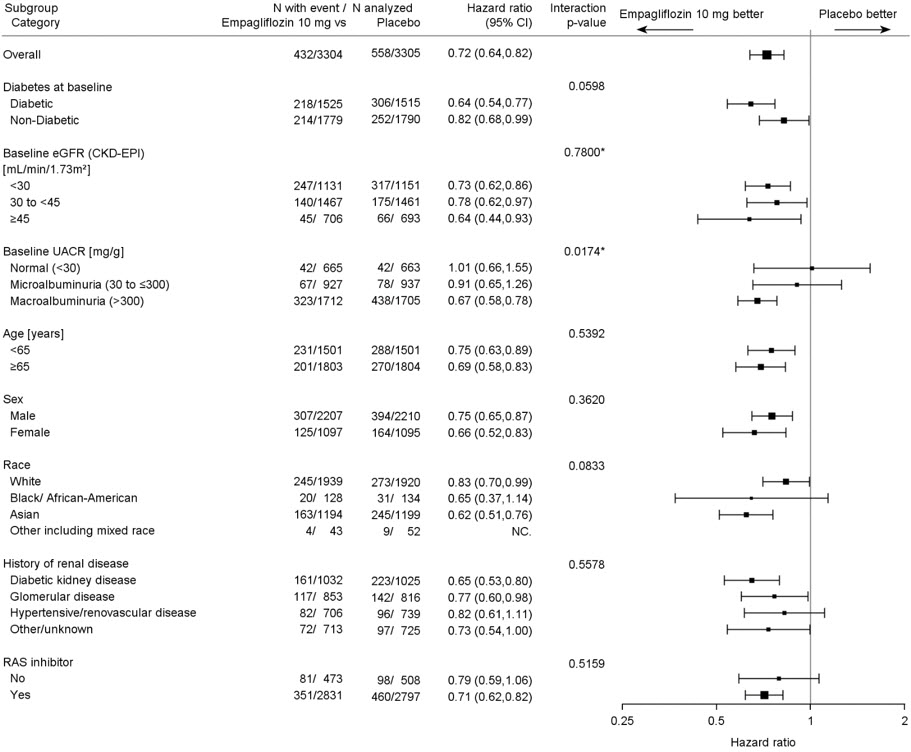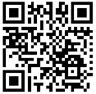 DRUG LABEL: Jardiance
NDC: 55154-0411 | Form: TABLET, FILM COATED
Manufacturer: Cardinal Health 107, LLC
Category: prescription | Type: HUMAN PRESCRIPTION DRUG LABEL
Date: 20260217

ACTIVE INGREDIENTS: EMPAGLIFLOZIN 10 mg/1 1
INACTIVE INGREDIENTS: SILICON DIOXIDE; CROSCARMELLOSE SODIUM; HYDROXYPROPYL CELLULOSE, UNSPECIFIED; LACTOSE MONOHYDRATE; MAGNESIUM STEARATE; MICROCRYSTALLINE CELLULOSE; FERRIC OXIDE YELLOW; HYPROMELLOSE, UNSPECIFIED; POLYETHYLENE GLYCOL, UNSPECIFIED; TALC; TITANIUM DIOXIDE

HIGHLIGHTS OF PRESCRIBING INFORMATION

These highlights do not include all the information needed to use JARDIANCE safely and effectively. See full prescribing information for JARDIANCE.
JARDIANCE® (empagliflozin tablets), for oral use
Initial U.S. Approval: 2014

RECENT MAJOR CHANGES

Warnings and Precautions (5.3) | 10/2025

1 INDICATIONS AND USAGE

JARDIANCE is a sodium-glucose co-transporter 2 (SGLT2) inhibitor indicated:

- To reduce the risk of cardiovascular death and hospitalization for heart failure in adults with heart failure. (1)
- To reduce the risk of sustained decline in eGFR, end-stage kidney disease, cardiovascular death, and hospitalization in adults with chronic kidney disease at risk of progression. (1)
- To reduce the risk of cardiovascular death in adults with type 2 diabetes mellitus and established cardiovascular disease. (1)
- As an adjunct to diet and exercise to improve glycemic control in adults and pediatric patients aged 10 years and older with type 2 diabetes mellitus. (1)

Limitations of Use:

- Not recommended for use to improve glycemic control in patients with type 1 diabetes mellitus. It may increase the risk of diabetic ketoacidosis in these patients. (1)
- Not recommended for use to improve glycemic control in patients with type 2 diabetes mellitus with an eGFR less than 30 mL/min/1.73 m^2. (1)
- Not recommended for the treatment of chronic kidney disease in patients with polycystic kidney disease or patients requiring or with a recent history of intravenous immunosuppressive therapy or greater than 45 mg of prednisone or equivalent for kidney disease. JARDIANCE is not expected to be effective in these populations. (1)

2 DOSAGE AND ADMINISTRATION

- Assess renal function before initiating and as clinically indicated. Assess volume status and correct volume depletion before initiating. (2.1)
- Recommended dosage is 10 mg orally once daily in the morning, taken with or without food. (2.2)
- For additional glycemic control, dosage may be increased to 25 mg orally once daily in patients tolerating JARDIANCE. (2.2)
- Withhold JARDIANCE for at least 3 days, if possible, prior to surgery or procedures associated with prolonged fasting. (2.3)

3 DOSAGE FORMS AND STRENGTHS

Tablets: 10 mg, 25 mg (3)

4 CONTRAINDICATIONS

- Hypersensitivity to empagliflozin or any of the excipients in JARDIANCE. (4)

5 WARNINGS AND PRECAUTIONS

- Diabetic Ketoacidosis in Patients with Type 1 Diabetes Mellitus and Other Ketoacidosis: Consider ketone monitoring in patients with type 1 diabetes mellitus and consider ketone monitoring in others at risk for ketoacidosis, as indicated. Assess for ketoacidosis regardless of presenting blood glucose levels and discontinue JARDIANCE if ketoacidosis is suspected. Monitor patients for resolution of ketoacidosis before restarting. (5.1)
- Volume Depletion: Before initiating JARDIANCE, assess volume status and renal function in patients with impaired renal function, elderly patients, or patients on loop diuretics. Monitor for signs and symptoms during therapy. (5.2)
- Genitourinary Infections, including Urosepsis, Pyelonephritis, Necrotizing Fasciitis of the Perineum (Fournier's Gangrene), and Genital Mycotic Infections: Monitor patients for signs and symptoms of genitourinary infections and treat promptly, if indicated. Immediately evaluate patients presenting with pain or tenderness, erythema, or swelling in the genital or perineal area, along with fever or malaise, for necrotizing fasciitis and if suspected, discontinue JARDIANCE, and promptly institute appropriate medical and/or surgical intervention. (5.3)
- Hypoglycemia: Adult patients taking an insulin secretagogue or insulin may have an increased risk of hypoglycemia. In pediatric patients 10 years of age and older, the risk of hypoglycemia was higher regardless of insulin use. Consider lowering the dosage of insulin secretagogue or insulin to reduce the risk of hypoglycemia when initiating JARDIANCE. (5.4)
- Lower Limb Amputation: Monitor patients for infections or ulcers of lower limbs, and institute appropriate treatment (5.5)
- Hypersensitivity Reactions: Serious hypersensitivity reactions (e.g., angioedema) have occurred with JARDIANCE. If hypersensitivity reactions occur, discontinue JARDIANCE, treat promptly, and monitor until signs and symptoms resolve. (5.6)

6 ADVERSE REACTIONS

Most common adverse reactions (5% or greater incidence) were urinary tract infections and female genital mycotic infections (6.1)

To report SUSPECTED ADVERSE REACTIONS, contact Boehringer Ingelheim Pharmaceuticals, Inc. at 1-800-542-6257 or FDA at 1-800-FDA-1088 or www.fda.gov/medwatch.

7 DRUG INTERACTIONS

See full prescribing information for information on drug interactions and interference of JARDIANCE with laboratory tests. (7)

8 USE IN SPECIFIC POPULATIONS

- Pregnancy: Advise females of the potential risk to a fetus especially during the second and third trimesters. (8.1)
- Lactation: Not recommended when breastfeeding. (8.2)
- Geriatric Patients: Higher incidence of adverse reactions related to volume depletion and reduced renal function. (8.5)
- Renal Impairment: Higher incidence of adverse reactions related to reduced renal function. (8.6)

FULL PRESCRIBING INFORMATION

1 INDICATIONS AND USAGE

JARDIANCE is indicated:

- to reduce the risk of cardiovascular death and hospitalization for heart failure in adults with heart failure.
- to reduce the risk of sustained decline in eGFR, end-stage kidney disease, cardiovascular death, and hospitalization in adults with chronic kidney disease at risk of progression.
- to reduce the risk of cardiovascular death in adults with type 2 diabetes mellitus and established cardiovascular disease.
- as an adjunct to diet and exercise to improve glycemic control in adults and pediatric patients aged 10 years and older with type 2 diabetes mellitus.

Limitations of Use

JARDIANCE is not recommended for use to improve glycemic control in patients with type 1 diabetes mellitus. It may increase the risk of diabetic ketoacidosis in these patients [see Warnings and Precautions (5.1)].

JARDIANCE is not recommended for use to improve glycemic control in patients with type 2 diabetes mellitus with an eGFR less than 30 mL/min/1.73 m^2. JARDIANCE is likely to be ineffective in this setting based upon its mechanism of action.

JARDIANCE is not recommended for the treatment of chronic kidney disease in patients with polycystic kidney disease or patients requiring or with a recent history of intravenous immunosuppressive therapy or greater than 45 mg of prednisone or equivalent for kidney disease [see Clinical Studies (14.5)]. JARDIANCE is not expected to be effective in these populations.

2 DOSAGE AND ADMINISTRATION

2.1 Testing Prior to Initiation of JARDIANCE

- Assess renal function before initiating JARDIANCE and as clinically indicated [see Warnings and Precautions (5.2)].
  - Use for glycemic control is not recommended in patients with an eGFR less than 30 mL/min/1.73 m^2 [see Use in Specific Populations (8.6)].
- Assess volume status. In patients with volume depletion, correct this condition before initiating JARDIANCE [see Warnings and Precautions (5.2) and Use in Specific Populations (8.5, 8.6)].

2.2 Recommended Dosage

Table 1 presents the recommended dosage of JARDIANCE in adult and pediatric patients aged 10 years and older.

Table 1 Recommended Dosage of JARDIANCE
Population | Indication | Recommended Dosage
Adults | Reduce the risk of cardiovascular death and hospitalization in patients with heart failure | - 10 mg orally once daily in the morning, taken with or without food.
Adults | Reduce the risk of sustained decline in eGFR, end-stage kidney disease, cardiovascular death, and hospitalization in adults with chronic kidney disease at risk of progression. | - 10 mg orally once daily in the morning, taken with or without food.
Adults | Reduce the risk of cardiovascular death in patients with type 2 diabetes mellitus with established cardiovascular disease | - 10 mg orally once daily in the morning, taken with or without food.
Adults | Glycemic control in type 2 diabetes mellitus | - 10 mg orally once daily in the morning, taken with or without food. - For additional glycemic control, may increase to 25 mg orally once daily in patients tolerating 10 mg once daily.
Pediatric patients aged 10 years and older | Glycemic control in type 2 diabetes mellitus | - 10 mg orally once daily in the morning, taken with or without food. - For additional glycemic control, may increase to 25 mg orally once daily in patients tolerating 10 mg once daily.

2.3 Temporary Interruption for Surgery

Withhold JARDIANCE for at least 3 days, if possible, prior to surgery or procedures associated with prolonged fasting. Resume JARDIANCE when the patient is clinically stable and has resumed oral intake [see Warnings and Precautions (5.1) and Clinical Pharmacology (12.2)].

2.4 Recommendations Regarding Missed Dose

- If a dose is missed, instruct patients to take the dose as soon as possible.
- Advise patients not to double up the next dose.

3 DOSAGE FORMS AND STRENGTHS

JARDIANCE tablets available as:

- 10 mg pale yellow, round, biconvex and bevel-edged, film-coated tablets debossed with "S 10" on one side and the Boehringer Ingelheim company symbol on the other side.
- 25 mg pale yellow, oval, biconvex, film-coated tablets debossed with "S 25" on one side and the Boehringer Ingelheim company symbol on the other side.

4 CONTRAINDICATIONS

JARDIANCE is contraindicated in patients:

- with a hypersensitivity to empagliflozin or any of the excipients in JARDIANCE, reactions such as angioedema have occurred [see Warnings and Precautions (5.6)].

5 WARNINGS AND PRECAUTIONS

5.1 Diabetic Ketoacidosis in Patients with Type 1 Diabetes Mellitus and Other Ketoacidosis

In patients with type 1 diabetes mellitus, JARDIANCE significantly increases the risk of diabetic ketoacidosis, a life-threatening event, beyond the background rate. In placebo-controlled trials of patients with type 1 diabetes mellitus, the risk of ketoacidosis was markedly increased in patients who received sodium glucose co-transporter 2 (SGLT2) inhibitors compared to patients who received placebo and fatal ketoacidosis has occurred with JARDIANCE. JARDIANCE is not indicated for glycemic control in patients with type 1 diabetes mellitus.

Type 2 diabetes mellitus and pancreatic disorders (e.g., history of pancreatitis or pancreatic surgery) are also risk factors for ketoacidosis. There have been postmarketing reports of fatal events of ketoacidosis in patients with type 2 diabetes mellitus using SGLT2 inhibitors, including JARDIANCE.

Precipitating conditions for diabetic ketoacidosis or other ketoacidosis include under-insulinization due to insulin dose reduction or missed insulin doses, acute febrile illness, reduced caloric intake, ketogenic diet, surgery, volume depletion, and alcohol abuse.

Signs and symptoms are consistent with dehydration and severe metabolic acidosis and include nausea, vomiting, abdominal pain, generalized malaise, and shortness of breath. Blood glucose levels at presentation may be below those typically expected for diabetic ketoacidosis (e.g., less than 250 mg/dL). Ketoacidosis and glucosuria may persist longer than typically expected. Urinary glucose excretion persists for 3 days after discontinuing JARDIANCE [see Clinical Pharmacology (12.2)]; however, there have been postmarketing reports of ketoacidosis and/or glucosuria lasting greater than 6 days and some up to 2 weeks after discontinuation of SGLT2 inhibitors.

Consider ketone monitoring in patients with type 1 diabetes mellitus and consider ketone monitoring in others at risk for ketoacidosis if indicated by the clinical situation. Assess for ketoacidosis regardless of presenting blood glucose levels in patients who present with signs and symptoms consistent with severe metabolic acidosis. If ketoacidosis is suspected, discontinue JARDIANCE, promptly evaluate, and treat ketoacidosis, if confirmed. Monitor patients for resolution of ketoacidosis before restarting JARDIANCE.

Withhold JARDIANCE, if possible, in temporary clinical situations that could predispose patients to ketoacidosis. Resume JARDIANCE when the patient is clinically stable and has resumed oral intake [see Dosage and Administration (2.3)].

Educate all patients on the signs and symptoms of ketoacidosis and instruct patients to discontinue JARDIANCE and seek medical attention immediately if signs and symptoms occur.

5.2 Volume Depletion

JARDIANCE can cause intravascular volume depletion which may sometimes manifest as symptomatic hypotension or acute transient changes in creatinine [see Adverse Reactions (6.1)]. There have been post-marketing reports of acute kidney injury, some requiring hospitalization and dialysis, in patients with type 2 diabetes mellitus receiving SGLT2 inhibitors, including JARDIANCE. Patients with impaired renal function (eGFR less than 60 mL/min/1.73 m^2), elderly patients, or patients on loop diuretics may be at increased risk for volume depletion or hypotension. Before initiating JARDIANCE in patients with one or more of these characteristics, assess volume status and renal function. In patients with volume depletion, correct this condition before initiating JARDIANCE. Monitor for signs and symptoms of volume depletion, and renal function after initiating therapy.

5.3 Genitourinary Infections, including Urosepsis, Pyelonephritis, Necrotizing Fasciitis of the Perineum (Fournier's Gangrene), and Genital Mycotic Infections

JARDIANCE increases urinary glucose excretion [see Clinical Pharmacology (12.2)] and increases the risk of genitourinary infections including urinary tract infections and genital mycotic infections in both male and female patients [see Adverse Reactions (6.1)].

Serious genitourinary infections, including urosepsis, pyelonephritis, and necrotizing fasciitis of the perineum (Fournier's gangrene, a rare life-threatening infection requiring urgent surgical intervention), have occurred in patients with and without diabetes mellitus receiving SGLT2 inhibitors, including JARDIANCE [see Adverse Reactions (6.2)]. Cases have required hospitalization. In patients with Fournier's gangrene, serious outcomes have included multiple surgeries and death.

Patients with a history of chronic or recurrent genitourinary infections are more likely to develop genitourinary infections when using JARDIANCE. Monitor patients for signs and symptoms of genitourinary infections and treat promptly, if indicated.

Immediately evaluate patients presenting with pain or tenderness, erythema, or swelling in the genital or perineal area, along with fever or malaise, for necrotizing fasciitis. If suspected, discontinue JARDIANCE and promptly institute appropriate medical and/or surgical intervention.

5.4 Hypoglycemia

Insulin and insulin secretagogues are known to cause hypoglycemia. In adult patients, the risk of hypoglycemia may be increased when JARDIANCE is used in combination with insulin secretagogues (e.g., sulfonylurea) or insulin. In pediatric patients aged 10 years and older, the risk of hypoglycemia was higher with JARDIANCE regardless of insulin use [see Adverse Reactions (6.1)].

The risk of hypoglycemia may be lowered by a reduction in the dose of sulfonylurea (or other concomitantly administered insulin secretagogues) or insulin. Inform patients using these concomitant medications and pediatric patients of the risk of hypoglycemia and educate them on the signs and symptoms of hypoglycemia.

5.5 Lower Limb Amputation

In some clinical studies with SGLT2 inhibitors an imbalance in the incidence of lower limb amputation has been observed. Across four JARDIANCE outcome trials, lower limb amputation event rates were 4.3 and 5.0 events per 1,000 patient-years in the placebo group and the JARDIANCE 10 mg or 25 mg dose group, respectively, with a HR of 1.05 (95 % CI) (0.81, 1.36).

In a long-term cardio-renal outcome trial [see Clinical Studies 14.5], in patients with chronic kidney disease, the occurrence of lower limb amputations was reported with event rates of 2.9, and 4.3 events per 1,000 patient-years in the placebo, and JARDIANCE 10 mg treatment arms, respectively. Amputation of the toe and mid-foot were most frequent (21 out of 28 JARDIANCE 10 mg treated patients with lower limb amputations), and some involving above and below the knee. Some patients had multiple amputations.

Peripheral artery disease, and diabetic foot infection (including osteomyelitis), were the most common precipitating medical events leading to the need for an amputation. The risk of amputation was highest in patients with a baseline history of diabetic foot, peripheral artery disease (including previous amputation) or diabetes.

Counsel patients about the importance of routine preventative foot care. Monitor patients receiving JARDIANCE for signs and symptoms of diabetic foot infection (including osteomyelitis), new pain or tenderness, sores or ulcers involving the lower limbs, and institute appropriate treatment.

5.6 Hypersensitivity Reactions

There have been postmarketing reports of serious hypersensitivity reactions (e.g., angioedema) in patients treated with JARDIANCE. If a hypersensitivity reaction occurs, discontinue JARDIANCE; treat promptly per standard of care, and monitor until signs and symptoms resolve. JARDIANCE is contraindicated in patients with hypersensitivity to empagliflozin or any of the excipients in JARDIANCE [see Contraindications (4)].

6 ADVERSE REACTIONS

The following important adverse reactions are described below and elsewhere in the labeling:

- Diabetic Ketoacidosis in Patients with Type 1 Diabetes Mellitus and Other Ketoacidosis [see Warnings and Precautions (5.1)]
- Volume Depletion [see Warnings and Precautions (5.2)]
- Genitourinary Infections, including Urosepsis, Pyelonephritis, Necrotizing Fasciitis of the Perineum (Fournier's Gangrene), and Genital Mycotic Infections [see Warnings and Precautions (5.3)]
- Hypoglycemia [see Warnings and Precautions (5.4)]
- Hypersensitivity Reactions [see Warnings and Precautions (5.6)]

6.1 Clinical Trials Experience

Because clinical trials are conducted under widely varying conditions, adverse reaction rates observed in the clinical trials of a drug cannot be directly compared to rates in the clinical trials of another drug and may not reflect the rates observed in practice.

JARDIANCE has been evaluated in clinical trials in adult and pediatric patients aged 10 to 17 years with type 2 diabetes mellitus, in adults with heart failure, and in adults with chronic kidney disease. The overall safety profile of JARDIANCE was generally consistent across the studied indications.

Clinical Trials in Adults with Type 2 Diabetes Mellitus

The data in Table 2 are derived from a pool of four 24-week placebo-controlled trials and 18-week data from a placebo-controlled trial with insulin in adult patients with type 2 diabetes mellitus. JARDIANCE was used as monotherapy in one trial and as add-on therapy in four trials [see Clinical Studies (14.1)].

These data reflect exposure of 1,976 adult patients to JARDIANCE with a mean exposure duration of approximately 23 weeks. Patients received placebo (N=995), JARDIANCE 10 mg (N=999), or JARDIANCE 25 mg (N=977) once daily. The mean age of the population was 56 years and 3% were older than 75 years of age. More than half (55%) of the population was male; 46% were White, 50% were Asian, and 3% were Black or African American. At baseline, 57% of the population had diabetes mellitus more than 5 years and had a mean hemoglobin A1c (HbA1c) of 8%. Established microvascular complications of diabetes mellitus at baseline included diabetic nephropathy (7%), retinopathy (8%), or neuropathy (16%). Baseline renal function was normal or mildly impaired in 91% of patients and moderately impaired in 9% of patients (mean eGFR 86.8 mL/min/1.73 m^2).

Table 2 shows adverse reactions (excluding hypoglycemia) that were not present at baseline, occurred more commonly in JARDIANCE-treated patients than on placebo and occurred in greater than or equal to 2% JARDIANCE-treated patients.

Table 2Adverse Reactions Reported in ≥2% of Adults with Type 2 Diabetes Mellitus Treated with JARDIANCE and Greater than Placebo in Pooled Placebo-Controlled Clinical Trials of JARDIANCE Monotherapy or Combination Therapy
Adverse Reactions | Placebo (%) N=995 | JARDIANCE 10 mg (%) N=999 | JARDIANCE 25 mg (%) N=977
Urinary tract infectiona | 7.6 | 9.3 | 7.6
Female genital mycotic infectionsb | 1.5 | 5.4 | 6.4
Upper respiratory tract infection | 3.8 | 3.1 | 4.0
Increased urinationc | 1.0 | 3.4 | 3.2
Dyslipidemia | 3.4 | 3.9 | 2.9
Arthralgia | 2.2 | 2.4 | 2.3
Male genital mycotic infectionsd | 0.4 | 3.1 | 1.6
Nausea | 1.4 | 2.3 | 1.1
aPredefined adverse event grouping, including, but not limited to, urinary tract infection, asymptomatic bacteriuria, cystitis
bFemale genital mycotic infections include the following adverse reactions: vulvovaginal mycotic infection, vaginal infection, vulvitis, vulvovaginal candidiasis, genital infection, genital candidiasis, genital infection fungal, genitourinary tract infection, vulvovaginitis, cervicitis, urogenital infection fungal, vaginitis bacterial. Percentages calculated with the number of female subjects in each group as denominator: placebo (N=481), JARDIANCE 10 mg (N=443), JARDIANCE 25 mg (N=420).
cPredefined adverse event grouping, including, but not limited to, polyuria, pollakiuria, and nocturia
dMale genital mycotic infections include the following adverse reactions: balanoposthitis, balanitis, genital infections fungal, genitourinary tract infection, balanitis candida, scrotal abscess, penile infection. Percentages calculated with the number of male subjects in each group as denominator: placebo (N=514), JARDIANCE 10 mg (N=556), JARDIANCE 25 mg (N=557).

Thirst (including polydipsia) was reported in 0%, 1.7%, and 1.5% for placebo, JARDIANCE 10 mg, and JARDIANCE 25 mg, respectively.

Volume Depletion

JARDIANCE causes an osmotic diuresis, which may lead to intravascular volume contraction and adverse reactions related to volume depletion. In the pool of five placebo-controlled clinical trials in adults, adverse reactions related to volume depletion (e.g., blood pressure (ambulatory) decreased, blood pressure systolic decreased, dehydration, hypotension, hypovolemia, orthostatic hypotension, and syncope) were reported by 0.3%, 0.5%, and 0.3% of patients treated with placebo, JARDIANCE 10 mg, and JARDIANCE 25 mg, respectively. JARDIANCE may increase the risk of hypotension in patients at risk for volume contraction [see Use in Specific Populations (8.5, 8.6)].

Increased Urination

In the pool of five placebo-controlled clinical trials in adults, adverse reactions of increased urination (e.g., polyuria, pollakiuria, and nocturia) occurred more frequently on JARDIANCE than on placebo (see Table 2). Specifically, nocturia was reported by 0.4%, 0.3%, and 0.8% of patients treated with placebo, JARDIANCE 10 mg, and JARDIANCE 25 mg, respectively.

Hypoglycemia in Clinical Trials for Glycemic Control in Adults with Type 2 Diabetes Mellitus

The incidence of hypoglycemia in adults by trial is shown in Table 3. The incidence of hypoglycemia increased when JARDIANCE was administered with insulin or sulfonylurea.

Table 3Incidence of Overalla and Severeb Hypoglycemic Events in Placebo-Controlled Clinical Trials for Glycemic Control in Adults with Type 2 Diabetes Mellitusc
Monotherapy (24 weeks) | Placebo (n=229) | JARDIANCE 10 mg (n=224) | JARDIANCE 25 mg (n=223)
Overall (%) | 0.4 | 0.4 | 0.4
Severe (%) | 0 | 0 | 0
In Combination with Metformin (24 weeks) | Placebo + Metformin (n=206) | JARDIANCE 10 mg + Metformin (n=217) | JARDIANCE 25 mg + Metformin (n=214)
Overall (%) | 0.5 | 1.8 | 1.4
Severe (%) | 0 | 0 | 0
In Combination with Metformin + Sulfonylurea (24 weeks) | Placebo (n=225) | JARDIANCE 10 mg + Metformin + Sulfonylurea (n=224) | JARDIANCE 25 mg + Metformin + Sulfonylurea (n=217)
Overall (%) | 8.4 | 16.1 | 11.5
Severe (%) | 0 | 0 | 0
In Combination with Pioglitazone +/- Metformin (24 weeks) | Placebo (n=165) | JARDIANCE 10 mg + Pioglitazone +/- Metformin (n=165) | JARDIANCE 25 mg + Pioglitazone +/- Metformin (n=168)
Overall (%) | 1.8 | 1.2 | 2.4
Severe (%) | 0 | 0 | 0
In Combination with Basal Insulin +/- Metformin (18 weeksd) | Placebo (n=170) | JARDIANCE 10 mg (n=169) | JARDIANCE 25 mg (n=155)
Overall (%) | 20.6 | 19.5 | 28.4
Severe (%) | 0 | 0 | 1.3
In Combination with MDI Insulin +/-Metformin (18 weeksd) | Placebo (n=188) | JARDIANCE 10 mg (n=186) | JARDIANCE 25 mg (n=189)
Overall (%) | 37.2 | 39.8 | 41.3
Severe (%) | 0.5 | 0.5 | 0.5
aOverall hypoglycemic events: plasma or capillary glucose of less than or equal to 70 mg/dL
bSevere hypoglycemic events: requiring assistance regardless of blood glucose
cTreated set (patients who had received at least one dosage of trial drug)
dInsulin dosage could not be adjusted during the initial 18-week treatment period

Other Adverse Reactions in Clinical Trials for Glycemic Control in Adults with Type 2 Diabetes Mellitus

- Genital Mycotic Infections: In the pool of five placebo-controlled clinical trials in adults, the incidence of genital mycotic infections (e.g., vaginal mycotic infection, vaginal infection, genital infection fungal, vulvovaginal candidiasis, and vulvitis) was increased in patients treated with JARDIANCE compared to placebo, occurring in 0.9%, 4.1%, and 3.7% of patients randomized to placebo, JARDIANCE 10 mg, and JARDIANCE 25 mg, respectively. Discontinuation from trial due to genital infection occurred in 0% of placebo-treated patients and 0.2% of patients treated with either JARDIANCE 10 mg or 25 mg.
  Genital mycotic infections occurred more frequently in female than male patients (see Table 2).
  Phimosis occurred more frequently in male patients treated with JARDIANCE 10 mg (less than 0.1%) and JARDIANCE 25 mg (0.1%) than placebo (0%).
- Urinary Tract Infections: In the pool of five placebo-controlled clinical trials in adults, the incidence of urinary tract infections (e.g., urinary tract infection, asymptomatic bacteriuria, and cystitis) was increased in patients treated with JARDIANCE compared to placebo (see Table 2). Patients with a history of chronic or recurrent urinary tract infections were more likely to experience a urinary tract infection. The rate of treatment discontinuation due to urinary tract infections was 0.1%, 0.2%, and 0.1% for placebo, JARDIANCE 10 mg, and JARDIANCE 25 mg, respectively.
  Urinary tract infections occurred more frequently in female patients. The incidence of urinary tract infections in female patients randomized to placebo, JARDIANCE 10 mg, and JARDIANCE 25 mg was 16.6%, 18.4%, and 17.0%, respectively. The incidence of urinary tract infections in male patients randomized to placebo, JARDIANCE 10 mg, and JARDIANCE 25 mg was 3.2%, 3.6%, and 4.1%, respectively [see Use in Specific Populations (8.5)].

Clinical Trial in Pediatric Patients Aged 10 to 17 Years with Type 2 Diabetes Mellitus

JARDIANCE was administered to 52 patients in a trial of 157 pediatric patients aged 10 to 17 years with type 2 diabetes mellitus with a mean exposure to JARDIANCE of 23.8 weeks [see Clinical Studies (14.2)]. Background therapies as adjunct to diet and exercise included metformin (51%), a combination of metformin and insulin (40.1%), insulin (3.2%), or none (5.7%). The mean HbA1c at baseline was 8.0% and the mean duration of type 2 diabetes mellitus was 2.1 years. The mean age was 14.5 years (range: 10-17 years) and 51.6% were aged 15 years and older. Approximately, 50% were White, 6% were Asian, 31% were Black or African American, and 38% were of Hispanic or Latino ethnicity. The mean BMI was 36.0 kg/m^2 and mean BMI Z-score was 3.0. Approximately 25% of the trial population had microalbuminuria or macroalbuminuria.

The risk of hypoglycemia was higher in pediatric patients treated with JARDIANCE regardless of concomitant insulin use. Hypoglycemia, defined as a blood glucose <54 mg/dL, occurred in 10 (19.2%) patients and in 4 (7.5%) patients treated with JARDIANCE and placebo, respectively. No severe hypoglycemic events occurred (severe hypoglycemia was defined as an event requiring the assistance of another person to actively administer carbohydrates, glucagon or take other corrective actions).

Clinical Trials in Adults with Heart Failure

No new adverse reactions were identified in EMPEROR-Reduced or EMPEROR-Preserved heart failure trials.

Clinical Trial in Adults with Chronic Kidney Disease

The safety profile in patients with chronic kidney disease was generally consistent with that observed across the studied indications. In a long-term cardio-renal outcome trial [see Clinical Studies 14.5], in patients with chronic kidney disease, the occurrence of lower limb amputations was reported with event rates of 2.9, and 4.3 events per 1,000 patient-years in the placebo, and JARDIANCE 10 mg treatment arms, respectively [see Warnings and Precautions (5.5)].

Laboratory Test Abnormalities in Clinical Trials

Increases in Serum Creatinine and Decreases in eGFR

Initiation of JARDIANCE causes an increase in serum creatinine and decrease in eGFR within weeks of starting therapy and then these changes stabilize. In a trial of adults with moderate renal impairment, larger mean changes were observed. In a long-term cardiovascular outcomes trial, the increase in serum creatinine and decrease in eGFR generally did not exceed 0.1 mg/dL and -9.0 mL/min/1.73 m^2, respectively, at Week 4, and reversed after treatment discontinuation, suggesting acute hemodynamic changes may play a role in the renal function changes observed with JARDIANCE.

Increase in Low-Density Lipoprotein Cholesterol (LDL-C)

Dose-related increases in low-density lipoprotein cholesterol (LDL-C) were observed in adults treated with JARDIANCE. LDL-C increased by 2.3%, 4.6%, and 6.5% in patients treated with placebo, JARDIANCE 10 mg, and JARDIANCE 25 mg, respectively. The range of mean baseline LDL-C levels was 90.3 to 90.6 mg/dL across treatment groups.

Increase in Hematocrit

In a pool of four placebo-controlled trials in adults, median hematocrit decreased by 1.3% in placebo and increased by 2.8% in JARDIANCE 10 mg and 2.8% in JARDIANCE 25 mg treated patients. At the end of treatment, 0.6%, 2.7%, and 3.5% of patients with hematocrits initially within the reference range had values above the upper limit of the reference range with placebo, JARDIANCE 10 mg, and JARDIANCE 25 mg, respectively.

6.2 Postmarketing Experience

Additional adverse reactions have been identified during postapproval use of JARDIANCE. Because these reactions are reported voluntarily from a population of uncertain size, it is generally not possible to reliably estimate their frequency or establish a causal relationship to drug exposure.

Gastrointestinal Disorders: Constipation
Infections: Necrotizing fasciitis of the perineum (Fournier's gangrene), urosepsis and pyelonephritis
Metabolism and Nutrition Disorders: Ketoacidosis
Renal and Urinary Disorders: Acute kidney injury
Skin and Subcutaneous Tissue Disorders: Angioedema, skin reactions (e.g., rash, urticaria)

7 DRUG INTERACTIONS

See Table 4 for clinically relevant interactions with JARDIANCE.

Table 4Clinically Relevant Interactions with JARDIANCE
Diuretics
Clinical Impact | Coadministration of empagliflozin with diuretics resulted in increased urine volume and frequency of voids, which might enhance the potential for volume depletion.
Intervention | Before initiating JARDIANCE, assess volume status and renal function. In patients with volume depletion, correct this condition before initiating JARDIANCE. Monitor for signs and symptoms of volume depletion, and renal function after initiating therapy.
Insulin or Insulin Secretagogues
Clinical Impact | The risk of hypoglycemia is increased when JARDIANCE is used in combination with insulin secretagogues (e.g., sulfonylurea) or insulin.
Intervention | Coadministration of JARDIANCE with an insulin secretagogue (e.g., sulfonylurea) or insulin may require lower dosages of the insulin secretagogue or insulin to reduce the risk of hypoglycemia.
Lithium
Clinical Impact | Concomitant use of an SGLT2 inhibitor with lithium may decrease serum lithium concentrations.
Intervention | Monitor serum lithium concentration more frequently during JARDIANCE initiation and dosage changes.
Positive Urine Glucose Test
Clinical Impact | SGLT2 inhibitors increase urinary glucose excretion and will lead to positive urine glucose tests.
Intervention | Monitoring glycemic control with urine glucose tests is not recommended in patients taking SGLT2 inhibitors. Use alternative methods to monitor glycemic control.
Interference with 1,5-anhydroglucitol (1,5-AG) Assay
Clinical Impact | Measurements of 1,5-AG are unreliable in assessing glycemic control in patients taking SGLT2 inhibitors.
Intervention | Monitoring glycemic control with 1,5-AG assay is not recommended. Use alternative methods to monitor glycemic control.

8 USE IN SPECIFIC POPULATIONS

8.1 Pregnancy

Risk Summary

Based on animal data showing adverse renal effects, JARDIANCE is not recommended during the second and third trimesters of pregnancy.

The limited available data with JARDIANCE in pregnant women are not sufficient to determine a drug-associated risk for major birth defects and miscarriage. There are risks to the mother and fetus associated with poorly controlled diabetes in pregnancy [see Clinical Considerations].

In animal studies, adverse renal changes were observed in rats when empagliflozin was administered during a period of renal development corresponding to the late second and third trimesters of human pregnancy. Doses approximately 13-times the maximum clinical dose caused renal pelvic and tubule dilatations that were reversible [see Data].

The estimated background risk of major birth defects is 6% to 10% in women with pre-gestational diabetes with a HbA1c >7 and has been reported to be as high as 20% to 25% in women with HbA1c >10. The estimated background risk of miscarriage for the indicated population is unknown. In the U.S. general population, the estimated background risk of major birth defects and miscarriage in clinically recognized pregnancies is 2% to 4% and 15% to 20%, respectively.

Clinical Considerations

Disease-associated maternal and/or embryo/fetal risk

Poorly controlled diabetes in pregnancy increases the maternal risk for diabetic ketoacidosis, pre-eclampsia, spontaneous abortions, preterm delivery, and delivery complications. Poorly controlled diabetes increases the fetal risk for major birth defects, stillbirth, and macrosomia related morbidity.

Data

Animal Data

Empagliflozin dosed directly to juvenile rats from postnatal day (PND) 21 until PND 90 at doses of 1, 10, 30, and 100 mg/kg/day caused increased kidney weights and renal tubular and pelvic dilatation at 100 mg/kg/day, which approximates 13-times the maximum clinical dose of 25 mg, based on AUC. These findings were not observed after a 13-week, drug-free recovery period. These outcomes occurred with drug exposure during periods of renal development in rats that correspond to the late second and third trimester of human renal development.

In embryo-fetal development studies in rats and rabbits, empagliflozin was administered for intervals coinciding with the first trimester period of organogenesis in humans. Doses up to 300 mg/kg/day, which approximates 48-times (rats) and 128-times (rabbits) the maximum clinical dose of 25 mg (based on AUC), did not result in adverse developmental effects. In rats, at higher doses of empagliflozin causing maternal toxicity, malformations of limb bones increased in fetuses at 700 mg/kg/day or 154-times the 25 mg maximum clinical dose. Empagliflozin crosses the placenta and reaches fetal tissues in rats. In the rabbit, higher doses of empagliflozin resulted in maternal and fetal toxicity at 700 mg/kg/day, or 139-times the 25 mg maximum clinical dose.

In pre- and postnatal development studies in pregnant rats, empagliflozin was administered from gestation day 6 through to lactation day 20 (weaning) at up to 100 mg/kg/day (approximately 16-times the 25 mg maximum clinical dose) without maternal toxicity. Reduced body weight was observed in the offspring at greater than or equal to 30 mg/kg/day (approximately 4-times the 25 mg maximum clinical dose).

8.2 Lactation

Risk Summary

There is limited information regarding the presence of JARDIANCE in human milk, the effects of JARDIANCE on the breastfed infant or the effects on milk production. Empagliflozin is present in the milk of lactating rats [see Data]. Since human kidney maturation occurs in utero and during the first 2 years of life when lactational exposure may occur, there may be risk to the developing human kidney.

Because of the potential for serious adverse reactions in a breastfed infant, including the potential for empagliflozin to affect postnatal renal development, advise patients that use of JARDIANCE is not recommended while breastfeeding.

Data

Empagliflozin was present at a low level in rat fetal tissues after a single oral dose to the dams at gestation day 18. In rat milk, the mean milk to plasma ratio ranged from 0.634 to 5, and was greater than one from 2 to 24 hours post-dose. The mean maximal milk to plasma ratio of 5 occurred at 8 hours post-dose, suggesting accumulation of empagliflozin in the milk. Juvenile rats directly exposed to empagliflozin showed a risk to the developing kidney (renal pelvic and tubular dilatations) during maturation.

8.4 Pediatric Use

The safety and effectiveness of JARDIANCE as an adjunct to diet and exercise to improve glycemic control in type 2 diabetes mellitus have been established in pediatric patients aged 10 years and older. Use of JARDIANCE for this indication is supported by evidence from a 26-week double-blind, placebo-controlled clinical trial, with a double-blind active treatment safety extension period of up to 52 weeks in 157 pediatric patients aged 10 to 17 years with type 2 diabetes mellitus and a pediatric pharmacokinetic study [see Clinical Pharmacology (12.3) and Clinical Studies (14.2)]. The safety profile of pediatric patients treated with JARDIANCE was similar to that observed in adults with type 2 diabetes mellitus, with the exception of hypoglycemia risk which was higher in pediatric patients treated with JARDIANCE regardless of concomitant insulin use [see Warnings and Precautions (5.4) and Adverse Reactions (6.1)].

The safety and effectiveness of JARDIANCE have not been established in pediatric patients less than 10 years of age as an adjunct to diet and exercise to improve glycemic control in type 2 diabetes mellitus.

The safety and effectiveness of JARDIANCE have not been established in pediatric patients to reduce the risk of:

- cardiovascular death and hospitalization for heart failure in patients with heart failure.
- sustained decline in eGFR, end-stage kidney disease, cardiovascular death, and hospitalization in patients with chronic kidney disease at risk of progression.
- cardiovascular death in patients with type 2 diabetes mellitus and established cardiovascular disease.

8.5 Geriatric Use

In glycemic control trials in patients with type 2 diabetes mellitus, a total of 2,721 (32%) patients treated with JARDIANCE were 65 years of age and older, and 491 (6%) were 75 years of age and older. JARDIANCE is expected to have diminished glycemic efficacy in elderly patients with renal impairment [see Use in Specific Populations (8.6)]. The risk of volume depletion-related adverse reactions increased in patients who were 75 years of age and older to 2.1%, 2.3%, and 4.4% for placebo, JARDIANCE 10 mg, and JARDIANCE 25 mg. The risk of urinary tract infections increased in patients who were 75 years of age and older to 10.5%, 15.7%, and 15.1% in patients randomized to placebo, JARDIANCE 10 mg, and JARDIANCE 25 mg, respectively [see Warnings and Precautions (5.2) and Adverse Reactions (6.1)].

In the EMPEROR-Reduced, EMPEROR-Preserved, and EMPA-KIDNEY trials, no overall differences in safety and effectiveness have been observed between patients 65 years of age and older and younger adult patients. EMPEROR-Reduced included 1,188 (64%) patients treated with JARDIANCE 65 years of age and older, and 503 (27%) patients 75 years of age and older. EMPEROR-Preserved included 2,403 (80%) patients treated with JARDIANCE 65 years of age and older, and 1,281 (43%) patients 75 years of age and older. EMPA-KIDNEY included 1,803 (55%) patients treated with JARDIANCE 65 years of age and older, and 758 (23%) patients 75 years of age and older.

8.6 Renal Impairment

The efficacy and safety of JARDIANCE for glycemic control were evaluated in a trial of adult patients with type 2 diabetes mellitus with mild and moderate renal impairment (eGFR 30 to less than 90 mL/min/1.73 m^2) [see Clinical Studies (14.1)]. In this trial, 195 adult patients exposed to JARDIANCE had an eGFR between 60 and 90 mL/min/1.73 m^2, 91 adult patients exposed to JARDIANCE had an eGFR between 45 and 60 mL/min/1.73 m^2, and 97 patients exposed to JARDIANCE had an eGFR between 30 and 45 mL/min/1.73 m^2. The glucose lowering benefit of JARDIANCE 25 mg decreased in adult patients with worsening renal function. The risks of renal impairment, volume depletion adverse reactions and urinary tract infection-related adverse reactions increased with worsening renal function [see Warnings and Precautions (5.2)]. Use of JARDIANCE for glycemic control in patients without established cardiovascular disease or cardiovascular risk factors is not recommended when eGFR is less than 30 mL/min/1.73 m^2.

JARDIANCE was evaluated in 7,020 adult patients with type 2 diabetes and established cardiovascular disease (eGFR greater than or equal to 30 mL/min/1.73 m^2) in the EMPA-REG OUTCOME trial, in a total of 9,718 patients with heart failure (eGFR greater than or equal to 20 mL/min/1.73 m^2) in the EMPEROR-Reduced and EMPEROR-Preserved trials, and in 6,609 adult patients with chronic kidney disease (eGFR 20 to 90 mL/min/1.73 m^2) in the EMPA-KIDNEY study. The safety profile across eGFR subgroups in these trials was consistent with the known safety profile [see Adverse Reactions (6.1) and Clinical Studies (14.3, 14.4, 14.5)].

Efficacy and safety trials with JARDIANCE did not enroll adult patients with an eGFR less than 20 mL/min/1.73 m^2 or on dialysis. Once enrolled, adult patients in the EMPA-REG OUTCOME, EMPEROR-Reduced, EMPEROR-Preserved, and EMPA-KIDNEY trials were not required to discontinue therapy for worsening of eGFR to less than 20 mL/min/1.73 m^2 or initiation of dialysis [see Clinical Studies (14.3, 14.4, 14.5)].

8.7 Hepatic Impairment

JARDIANCE may be used in patients with hepatic impairment [see Clinical Pharmacology (12.3)].

10 OVERDOSAGE

In the event of an overdose with JARDIANCE, consider contacting the Poison Help line (1-800-222-1222) or a medical toxicologist for additional overdosage management recommendations. Removal of empagliflozin by hemodialysis has not been studied.

11 DESCRIPTION

JARDIANCE tablets for oral use contain empagliflozin, an inhibitor of the SGLT2.

The chemical name of empagliflozin is D-Glucitol,1,5-anhydro-1-C-[4-chloro-3-[[4-[[(3S)-tetrahydro-3-furanyl]oxy]phenyl]methyl]phenyl]-, (1S).

Its molecular formula is C23H27ClO7 and the molecular weight is 450.91. The structural formula is:

Empagliflozin is a white to yellowish, non-hygroscopic powder. It is very slightly soluble in water, sparingly soluble in methanol, slightly soluble in ethanol and acetonitrile, soluble in 50% acetonitrile/water, and practically insoluble in toluene.

Each film-coated tablet of JARDIANCE contains 10 mg or 25 mg of empagliflozin (free base) and the following inactive ingredients: colloidal silicon dioxide, croscarmellose sodium, hydroxypropyl cellulose, lactose monohydrate, magnesium stearate, and microcrystalline cellulose. In addition, the film coating contains the following inactive ingredients: ferric oxide yellow, hypromellose, polyethylene glycol, talc, and titanium dioxide.

12 CLINICAL PHARMACOLOGY

12.1 Mechanism of Action

Empagliflozin is an inhibitor of SGLT2, the predominant transporter responsible for reabsorption of glucose from the glomerular filtrate back into the circulation. By inhibiting SGLT2, empagliflozin reduces renal reabsorption of filtered glucose and lowers the renal threshold for glucose, and thereby increases urinary glucose excretion.

Empagliflozin also reduces sodium reabsorption and increases the delivery of sodium to the distal tubule. This may influence several physiological functions including, but not restricted to, increasing tubuloglomerular feedback and reducing intraglomerular pressure, lowering both pre- and afterload of the heart and downregulating sympathetic activity.

12.2 Pharmacodynamics

Urinary Glucose Excretion

In patients with type 2 diabetes mellitus, urinary glucose excretion increased immediately following a dose of empagliflozin and was maintained at the end of a 4-week treatment period averaging at approximately 64 grams per day with 10 mg empagliflozin and 78 grams per day with 25 mg empagliflozin once daily [see Clinical Studies (14)]. Data from single oral doses of empagliflozin in healthy subjects indicate that, on average, the elevation in urinary glucose excretion approaches baseline by about 3 days for the 10 mg and 25 mg doses.

Urinary Volume

In a 5-day study, mean 24-hour urine volume increase from baseline was 341 mL on Day 1 and 135 mL on Day 5 of empagliflozin 25 mg once daily treatment.

Cardiac Electrophysiology

In a randomized, placebo-controlled, active-comparator, crossover study, 30 healthy subjects were administered a single oral dose of empagliflozin 25 mg, empagliflozin 200 mg (8 times the maximum dose), moxifloxacin, and placebo. No increase in QTc was observed with either 25 mg or 200 mg empagliflozin.

12.3 Pharmacokinetics

The pharmacokinetics of empagliflozin has been characterized in healthy volunteers and patients with type 2 diabetes mellitus and no clinically relevant differences were noted between the two populations. The steady-state mean plasma AUC and Cmax were 1,870 nmol∙h/L and 259 nmol/L, respectively, with 10 mg empagliflozin once daily treatment, and 4,740 nmol∙h/L and 687 nmol/L, respectively, with 25 mg empagliflozin once daily treatment. Systemic exposure of empagliflozin increased in a dose-proportional manner in the therapeutic dose range. Empagliflozin does not appear to have time-dependent pharmacokinetic characteristics. Following once-daily dosing, up to 22% accumulation, with respect to plasma AUC, was observed at steady-state.

Absorption

After oral administration, peak plasma concentrations of empagliflozin were reached at 1.5 hours post-dose. Administration of 25 mg empagliflozin after intake of a high-fat and high-calorie meal resulted in slightly lower exposure; AUC decreased by approximately 16% and Cmax decreased by approximately 37%, compared to fasted condition. The observed effect of food on empagliflozin pharmacokinetics was not considered clinically relevant and empagliflozin may be administered with or without food.

Distribution

The apparent steady-state volume of distribution was estimated to be 73.8 L based on a population pharmacokinetic analysis. Following administration of an oral [^14C]-empagliflozin solution to healthy subjects, the red blood cell partitioning was approximately 36.8% and plasma protein binding was 86.2%.

Elimination

The apparent terminal elimination half-life of empagliflozin was estimated to be 12.4 h and apparent oral clearance was 10.6 L/h based on the population pharmacokinetic analysis.

Metabolism

No major metabolites of empagliflozin were detected in human plasma and the most abundant metabolites were three glucuronide conjugates (2-O-, 3-O-, and 6-O-glucuronide). Systemic exposure of each metabolite was less than 10% of total drug-related material. In vitro studies suggested that the primary route of metabolism of empagliflozin in humans is glucuronidation by the uridine 5'-diphospho-glucuronosyltransferases UGT2B7, UGT1A3, UGT1A8, and UGT1A9.

Excretion

Following administration of an oral [^14C]-empagliflozin solution to healthy subjects, approximately 95.6% of the drug-related radioactivity was eliminated in feces (41.2%) or urine (54.4%). The majority of drug-related radioactivity recovered in feces was unchanged parent drug and approximately half of drug-related radioactivity excreted in urine was unchanged parent drug.

Specific Populations

Pediatric Patients

The pharmacokinetics and pharmacodynamics of empagliflozin were investigated in pediatric patients aged 10 to 17 years with type 2 diabetes mellitus. Oral administration of empagliflozin at 10 mg and 25 mg resulted in exposure within the range observed in adult patients.

Effects of Age, Body Mass Index, Gender, and Race

Age, body mass index (BMI), gender and race (Asians versus primarily Whites) do not have a clinically meaningful effect on pharmacokinetics of empagliflozin.

Patients with Hepatic Impairment

In adult patients with mild, moderate, and severe hepatic impairment according to the Child-Pugh classification, AUC of empagliflozin increased by approximately 23%, 47%, and 75%, and Cmax increased by approximately 4%, 23%, and 48%, respectively, compared to subjects with normal hepatic function.

Patients with Renal Impairment

In adult patients with type 2 diabetes mellitus with mild (eGFR: 60 to less than 90 mL/min/1.73 m^2), moderate (eGFR: 30 to less than 60 mL/min/1.73 m^2), and severe (eGFR: less than 30 mL/min/1.73 m^2) renal impairment and patients on dialysis due to kidney failure, AUC of empagliflozin increased by approximately 18%, 20%, 66%, and 48%, respectively, compared to subjects with normal renal function. Peak plasma levels of empagliflozin were similar in patients with moderate renal impairment and patients on dialysis due to kidney failure compared to subjects with normal renal function. Peak plasma levels of empagliflozin were roughly 20% higher in patients with mild and severe renal impairment as compared to patients with normal renal function. Population pharmacokinetic analysis showed that the apparent oral clearance of empagliflozin decreased, with a decrease in eGFR leading to an increase in drug exposure. However, the fraction of empagliflozin that was excreted unchanged in urine, and urinary glucose excretion, declined with decrease in eGFR.

Drug Interaction Studies

In vitro Assessment of Drug Interactions

Empagliflozin does not inhibit, inactivate, or induce CYP450 isoforms. In vitro data suggest that the primary route of metabolism of empagliflozin in humans is glucuronidation by the uridine 5'-diphospho-glucuronosyltransferases UGT1A3, UGT1A8, UGT1A9, and UGT2B7. Empagliflozin does not inhibit UGT1A1, UGT1A3, UGT1A8, UGT1A9, or UGT2B7. Therefore, no effect of empagliflozin is anticipated on concomitantly administered drugs that are substrates of the major CYP450 isoforms or UGT1A1, UGT1A3, UGT1A8, UGT1A9, or UGT2B7. The effect of UGT induction (e.g., induction by rifampicin or any other UGT enzyme inducer) on empagliflozin exposure has not been evaluated.

Empagliflozin is a substrate for P-glycoprotein (P-gp) and breast cancer resistance protein (BCRP), but it does not inhibit these efflux transporters at therapeutic doses. Based on in vitro studies, empagliflozin is considered unlikely to cause interactions with drugs that are P-gp substrates. Empagliflozin is a substrate of the human uptake transporters OAT3, OATP1B1, and OATP1B3, but not OAT1 and OCT2. Empagliflozin does not inhibit any of these human uptake transporters at clinically relevant plasma concentrations and, therefore, no effect of empagliflozin is anticipated on concomitantly administered drugs that are substrates of these uptake transporters.

In vivo Assessment of Drug Interactions

Empagliflozin pharmacokinetics were similar with and without coadministration of metformin, glimepiride, pioglitazone, sitagliptin, linagliptin, warfarin, verapamil, ramipril, and simvastatin in healthy volunteers and with or without coadministration of hydrochlorothiazide and torsemide in patients with type 2 diabetes mellitus (see Figure 1). In subjects with normal renal function, coadministration of empagliflozin with probenecid resulted in a 30% decrease in the fraction of empagliflozin excreted in urine without any effect on 24-hour urinary glucose excretion. The relevance of this observation to patients with renal impairment is unknown.

Figure 1 Effect of Various Medications on the Pharmacokinetics of Empagliflozin as Displayed as 90% Confidence Interval of Geometric Mean AUC and Cmax Ratios [reference lines indicate 100% (80% - 125%)]

aempagliflozin, 50 mg, once daily; bempagliflozin, 25 mg, single dose; cempagliflozin, 25 mg, once daily; dempagliflozin, 10 mg, single dose

Empagliflozin had no clinically relevant effect on the pharmacokinetics of metformin, glimepiride, pioglitazone, sitagliptin, linagliptin, warfarin, digoxin, ramipril, simvastatin, hydrochlorothiazide, torsemide, and oral contraceptives when coadministered in healthy volunteers (see Figure 2).

Figure 2 Effect of Empagliflozin on the Pharmacokinetics of Various Medications as Displayed as 90% Confidence Interval of Geometric Mean AUC and Cmax Ratios [reference lines indicate 100% (80% - 125%)]

aempagliflozin, 50 mg, once daily; bempagliflozin, 25 mg, once daily; cempagliflozin, 25 mg, single dose; dadministered as simvastatin; eadministered as warfarin racemic mixture; fadministered as Microgynon®; gadministered as ramipril

13 NONCLINICAL TOXICOLOGY

13.1 Carcinogenesis, Mutagenesis, Impairment of Fertility

Carcinogenesis

Carcinogenesis was evaluated in 2-year studies conducted in CD-1 mice and Wistar rats. Empagliflozin did not increase the incidence of tumors in female rats dosed at 100, 300, or 700 mg/kg/day (up to 72 times the exposure from the maximum clinical dose of 25 mg). In male rats, hemangiomas of the mesenteric lymph node were increased significantly at 700 mg/kg/day or approximately 42 times the exposure from a 25 mg clinical dose. Empagliflozin did not increase the incidence of tumors in female mice dosed at 100, 300, or 1,000 mg/kg/day (up to 62 times the exposure from a 25 mg clinical dose). Renal tubule adenomas and carcinomas were observed in male mice at 1,000 mg/kg/day, which is approximately 45 times the exposure of the maximum clinical dose of 25 mg. These tumors may be associated with a metabolic pathway predominantly present in the male mouse kidney.

Mutagenesis

Empagliflozin was not mutagenic or clastogenic with or without metabolic activation in the in vitro Ames bacterial mutagenicity assay, the in vitro L5178Y tk+/- mouse lymphoma cell assay, and an in vivo micronucleus assay in rats.

Impairment of Fertility

Empagliflozin had no effects on mating, fertility or early embryonic development in treated male or female rats up to the high dose of 700 mg/kg/day (approximately 155 times the 25 mg clinical dose in males and females, respectively).

14 CLINICAL STUDIES

14.1 Glycemic Control Trials in Adults with Type 2 Diabetes Mellitus

JARDIANCE has been studied as monotherapy and in combination with metformin, sulfonylurea, pioglitazone, linagliptin, and insulin. JARDIANCE has also been studied in patients with type 2 diabetes mellitus with mild or moderate renal impairment.

In adult patients with type 2 diabetes mellitus, treatment with JARDIANCE reduced hemoglobin A1c (HbA1c), compared to placebo. The reduction in HbA1c for JARDIANCE compared with placebo was observed across subgroups including sex, race, geographic region, baseline BMI and duration of disease.

Monotherapy

A total of 986 patients with type 2 diabetes mellitus participated in a double-blind, placebo-controlled trial to evaluate the efficacy of JARDIANCE monotherapy.

Treatment-naïve patients with inadequately controlled type 2 diabetes mellitus entered an open-label placebo run-in for 2 weeks. At the end of the run-in period, patients who remained inadequately controlled and had an HbA1c between 7% and 10% were randomized to placebo, JARDIANCE 10 mg, JARDIANCE 25 mg, or a reference comparator.

At Week 24, treatment with JARDIANCE 10 mg or 25 mg daily provided statistically significant reductions in HbA1c (p-value <0.0001), fasting plasma glucose (FPG), and body weight compared with placebo (see Table 5 and Figure 3).

Table 5Results at Week 24 From a Placebo-Controlled Monotherapy Trial of JARDIANCE
 | JARDIANCE 10 mg N=224 | JARDIANCE 25 mg N=224 | Placebo N=228
HbA1c (%)a
Baseline (mean) | 7.9 | 7.9 | 7.9
Change from baseline (adjusted mean) | -0.7 | -0.8 | 0.1
Difference from placebo (adjusted mean) (97.5% CI) | -0.7b (-0.9, -0.6) | -0.9b (-1.0, -0.7) | --
Patients [n (%)] achieving HbA1c <7% | 72 (35%) | 88 (44%) | 25 (12%)
FPG (mg/dL)c
Baseline (mean) | 153 | 153 | 155
Change from baseline (adjusted mean) | -19 | -25 | 12
Difference from placebo (adjusted mean) (95% CI) | -31 (-37, -26) | -36 (-42, -31) | --
Body Weight
Baseline (mean) in kg | 78 | 78 | 78
% change from baseline (adjusted mean) | -2.8 | -3.2 | -0.4
Difference from placebo (adjusted mean) (95% CI) | -2.5b (-3.1, -1.9) | -2.8b (-3.4, -2.2) | --
aModified intent-to-treat population. Last observation on trial (LOCF) was used to impute missing data at Week 24. At Week 24, 9.4%, 9.4%, and 30.7% was imputed for patients randomized to JARDIANCE 10 mg, JARDIANCE 25 mg, and placebo, respectively.
bANCOVA derived p-value <0.0001 (HbA1c: ANCOVA model includes baseline HbA1c, treatment, renal function, and region. Body weight and FPG: same model used as for HbA1c but additionally including baseline body weight/baseline FPG, respectively.)
cFPG (mg/dL); for JARDIANCE 10 mg, n=223, for JARDIANCE 25 mg, n=223, and for placebo, n=226

Figure 3 Adjusted Mean HbA1c Change at Each Time Point (Completers) and at Week 24 (mITT Population) - LOCF

At Week 24, the systolic blood pressure was statistically significantly reduced compared to placebo by -2.6 mmHg (placebo-adjusted, p-value=0.0231) in patients randomized to 10 mg of JARDIANCE and by -3.4 mmHg (placebo-corrected, p-value=0.0028) in patients randomized to 25 mg of JARDIANCE.

Add-On Combination Therapy with Metformin

A total of 637 patients with type 2 diabetes mellitus participated in a double-blind, placebo-controlled trial to evaluate the efficacy of JARDIANCE in combination with metformin.

Patients with type 2 diabetes mellitus inadequately controlled on at least 1,500 mg of metformin per day entered an open-label 2-week placebo run-in. At the end of the run-in period, patients who remained inadequately controlled and had an HbA1c between 7% and 10% were randomized to placebo, JARDIANCE 10 mg, or JARDIANCE 25 mg.

At Week 24, treatment with JARDIANCE 10 mg or 25 mg daily provided statistically significant reductions in HbA1c (p-value <0.0001), FPG, and body weight compared with placebo (see Table 6).

Table 6Results at Week 24 From a Placebo-Controlled Trial for JARDIANCE used in Combination with Metformin
 | JARDIANCE 10 mg N=217 | JARDIANCE 25 mg N=213 | Placebo N=207
HbA1c (%)a
Baseline (mean) | 7.9 | 7.9 | 7.9
Change from baseline (adjusted mean) | -0.7 | -0.8 | -0.1
Difference from placebo + metformin (adjusted mean) (95% CI) | -0.6b (-0.7, -0.4) | -0.6b (-0.8, -0.5) | --
Patients [n (%)] achieving HbA1c <7% | 75 (38%) | 74 (39%) | 23 (13%)
FPG (mg/dL)c
Baseline (mean) | 155 | 149 | 156
Change from baseline (adjusted mean) | -20 | -22 | 6
Difference from placebo + metformin (adjusted mean) | -26 | -29 | --
Body Weight
Baseline mean in kg | 82 | 82 | 80
% change from baseline (adjusted mean) | -2.5 | -2.9 | -0.5
Difference from placebo (adjusted mean) (95% CI) | -2.0b (-2.6, -1.4) | -2.5b (-3.1, -1.9) | --
aModified intent-to-treat population. Last observation on trial (LOCF) was used to impute missing data at Week 24. At Week 24, 9.7%, 14.1%, and 24.6% was imputed for patients randomized to JARDIANCE 10 mg, JARDIANCE 25 mg, and placebo, respectively.
bANCOVA p-value <0.0001 (HbA1c: ANCOVA model includes baseline HbA1c, treatment, renal function, and region. Body weight and FPG: same model used as for HbA1c but additionally including baseline body weight/baseline FPG, respectively.)
cFPG (mg/dL); for JARDIANCE 10 mg, n=216, for JARDIANCE 25 mg, n=213, and for placebo, n=207

At Week 24, the systolic blood pressure was statistically significantly reduced compared to placebo by -4.1 mmHg (placebo-corrected, p-value <0.0001) for JARDIANCE 10 mg and -4.8 mmHg (placebo-corrected, p-value <0.0001) for JARDIANCE 25 mg.

Initial Combination Therapy with Metformin

A total of 1,364 patients with type 2 diabetes mellitus participated in a double-blind, randomized, active-controlled trial to evaluate the efficacy of JARDIANCE in combination with metformin as initial therapy compared to the corresponding individual components.

Treatment-naïve patients with inadequately controlled type 2 diabetes mellitus entered an open-label placebo run-in for 2 weeks. At the end of the run-in period, patients who remained inadequately controlled and had an HbA1c between 7% and 10.5% were randomized to one of 8 active-treatment arms: JARDIANCE 10 mg or 25 mg; metformin 1,000 mg, or 2,000 mg; JARDIANCE 10 mg in combination with 1,000 mg or 2,000 mg metformin; or JARDIANCE 25 mg in combination with 1,000 mg or 2,000 mg metformin.

At Week 24, initial therapy of JARDIANCE in combination with metformin provided statistically significant reductions in HbA1c (p-value <0.01) compared to the individual components (see Table 7).

Table 7Glycemic Parameters at 24 Weeks in a Trial Comparing JARDIANCE and Metformin to the Individual Components as Initial Therapy
 | JARDIANCE 10 mg + Metformin 1,000 mga N=161 | JARDIANCE 10 mg + Metformin 2,000 mga N=167 | JARDIANCE 25 mg + Metformin 1,000 mga N=165 | JARDIANCE 25 mg + Metformin 2,000 mga N=169 | JARDIANCE 10 mg N=169 | JARDIANCE 25 mg N=163 | Metformin 1,000 mga N=167 | Metformin 2,000 mga N=162
HbA1c (%)
Baseline (mean) | 8.7 | 8.7 | 8.8 | 8.7 | 8.6 | 8.9 | 8.7 | 8.6
Change from baseline (adjusted mean) | -2.0 | -2.1 | -1.9 | -2.1 | -1.4 | -1.4 | -1.2 | -1.8
Comparison vs JARDIANCE (adjusted mean) (95% CI) | -0.6b (-0.9, -0.4) | -0.7b (-1.0, -0.5) | -0.6c (-0.8, -0.3) | -0.7c (-1.0, -0.5) | -- | -- | -- | --
Comparison vs metformin (adjusted mean) (95% CI) | -0.8b (-1.0, -0.6) | -0.3b (-0.6, -0.1) | -0.8c (-1.0, -0.5) | -0.3c (-0.6, -0.1) | -- | -- | -- | --
aMetformin total daily dose, administered in two equally divided doses per day.
bp-value ≤0.0062 (modified intent-to-treat population [observed case] MMRM model included treatment, renal function, region, visit, visit by treatment interaction, and baseline HbA1c).
cp-value ≤0.0056 (modified intent-to-treat population [observed case] MMRM model included treatment, renal function, region, visit, visit by treatment interaction, and baseline HbA1c).

Add-On Combination Therapy with Metformin and Sulfonylurea

A total of 666 patients with type 2 diabetes mellitus participated in a double-blind, placebo-controlled trial to evaluate the efficacy of JARDIANCE in combination with metformin plus a sulfonylurea.

Patients with inadequately controlled type 2 diabetes mellitus on at least 1,500 mg per day of metformin and on a sulfonylurea, entered a 2-week open-label placebo run-in. At the end of the run-in, patients who remained inadequately controlled and had an HbA1c between 7% and 10% were randomized to placebo, JARDIANCE 10 mg, or JARDIANCE 25 mg.

Treatment with JARDIANCE 10 mg or 25 mg daily provided statistically significant reductions in HbA1c (p-value <0.0001), FPG, and body weight compared with placebo (see Table 8).

Table 8Results at Week 24 from a Placebo-Controlled Trial for JARDIANCE in Combination with Metformin and Sulfonylurea
 | JARDIANCE 10 mg N=225 | JARDIANCE 25 mg N=216 | Placebo N=225
HbA1c (%)a
Baseline (mean) | 8.1 | 8.1 | 8.2
Change from baseline (adjusted mean) | -0.8 | -0.8 | -0.2
Difference from placebo (adjusted mean) (95% CI) | -0.6b (-0.8, -0.5) | -0.6b (-0.7, -0.4) | --
Patients [n (%)] achieving HbA1c <7% | 55 (26%) | 65 (32%) | 20 (9%)
FPG (mg/dL)c
Baseline (mean) | 151 | 156 | 152
Change from baseline (adjusted mean) | -23 | -23 | 6
Difference from placebo (adjusted mean) | -29 | -29 | --
Body Weight
Baseline mean in kg | 77 | 78 | 76
% change from baseline (adjusted mean) | -2.9 | -3.2 | -0.5
Difference from placebo (adjusted mean) (95% CI) | -2.4b (-3.0, -1.8) | -2.7b (-3.3, -2.1) | --
aModified intent-to-treat population. Last observation on trial (LOCF) was used to impute missing data at Week 24. At Week 24, 17.8%, 16.7%, and 25.3% was imputed for patients randomized to JARDIANCE 10 mg, JARDIANCE 25 mg, and placebo, respectively.
bANCOVA p-value <0.0001 (HbA1c: ANCOVA model includes baseline HbA1c, treatment, renal function, and region. Body weight and FPG: same model used as for HbA1c but additionally including baseline body weight/baseline FPG, respectively.)
cFPG (mg/dL); for JARDIANCE 10 mg, n=225, for JARDIANCE 25 mg, n=215, for placebo, n=224

In Combination with Linagliptin as Add-On to Metformin Therapy

A total of 686 patients with type 2 diabetes mellitus participated in a double-blind, active-controlled trial to evaluate the efficacy of JARDIANCE 10 mg or 25 mg in combination with linagliptin 5 mg compared to the individual components.

Patients with type 2 diabetes mellitus inadequately controlled on at least 1,500 mg of metformin per day entered a single-blind placebo run-in period for 2 weeks. At the end of the run-in period, patients who remained inadequately controlled and had an HbA1c between 7% and 10.5% were randomized 1:1:1:1:1 to one of 5 active-treatment arms of JARDIANCE 10 mg or 25 mg, linagliptin 5 mg, or linagliptin 5 mg in combination with 10 mg or 25 mg JARDIANCE as a fixed-dose combination tablet.

At Week 24, JARDIANCE 10 mg or 25 mg used in combination with linagliptin 5 mg provided statistically significant improvement in HbA1c (p-value <0.0001) and FPG (p-value <0.001) compared to the individual components in patients who had been inadequately controlled on metformin. Treatment with JARDIANCE/linagliptin 25 mg/5 mg or JARDIANCE/linagliptin 10 mg/5 mg daily also resulted in a statistically significant reduction in body weight compared to linagliptin 5 mg (p-value <0.0001). There was no statistically significant difference in body weight compared to JARDIANCE alone.

Active-Controlled Trial versus Glimepiride in Combination with Metformin

The efficacy of JARDIANCE was evaluated in a double-blind, glimepiride-controlled, trial in 1,545 patients with type 2 diabetes mellitus with insufficient glycemic control despite metformin therapy.

Patients with inadequate glycemic control and an HbA1c between 7% and 10% after a 2-week run-in period were randomized to glimepiride or JARDIANCE 25 mg.

At Week 52, JARDIANCE 25 mg and glimepiride lowered HbA1c and FPG (see Table 9, Figure 4). The difference in observed effect size between JARDIANCE 25 mg and glimepiride excluded the pre-specified non-inferiority margin of 0.3%. The mean daily dosage of glimepiride was 2.7 mg and the maximal approved dosage in the United States is 8 mg per day.

Table 9Results at Week 52 from an Active-Controlled Trial Comparing JARDIANCE to Glimepiride as Add-On Therapy in Patients Inadequately Controlled on Metformin
 | JARDIANCE 25 mg N=765 | Glimepiride N=780
HbA1c (%)a
Baseline (mean) | 7.9 | 7.9
Change from baseline (adjusted mean) | -0.7 | -0.7
Difference from glimepiride (adjusted mean) (97.5% CI) | -0.07b (-0.15, 0.01) | --
FPG (mg/dL)d
Baseline (mean) | 150 | 150
Change from baseline (adjusted mean) | -19 | -9
Difference from glimepiride (adjusted mean) | -11 | --
Body Weight
Baseline mean in kg | 82.5 | 83
% change from baseline (adjusted mean) | -3.9 | 2.0
Difference from glimepiride (adjusted mean) (95% CI) | -5.9c (-6.3, -5.5) | --
aModified intent-to-treat population. Last observation on trial (LOCF) was used to impute data missing at Week 52. At Week 52, data was imputed for 15.3% and 21.9% of patients randomized to JARDIANCE 25 mg and glimepiride, respectively.
bNon-inferior, ANCOVA model p-value <0.0001 (HbA1c: ANCOVA model includes baseline HbA1c, treatment, renal function, and region)
cANCOVA p-value <0.0001 (Body weight and FPG: same model used as for HbA1c but additionally including baseline body weight/baseline FPG, respectively.)
dFPG (mg/dL); for JARDIANCE 25 mg, n=764, for glimepiride, n=779

Figure 4 Adjusted mean HbA1c Change at Each Time Point (Completers) and at Week 52 (mITT Population) - LOCF

At Week 52, the adjusted mean change from baseline in systolic blood pressure was -3.6 mmHg, compared to 2.2 mmHg for glimepiride. The differences between treatment groups for systolic blood pressure was statistically significant (p-value <0.0001).

At Week 104, the adjusted mean change from baseline in HbA1c was -0.75% for JARDIANCE 25 mg and -0.66% for glimepiride. The adjusted mean treatment difference was -0.09% with a 97.5% confidence interval of (-0.32%, 0.15%), excluding the pre-specified non-inferiority margin of 0.3%. The mean daily dosage of glimepiride was 2.7 mg and the maximal approved dosage in the United States is 8 mg per day. The Week 104 analysis included data with and without concomitant glycemic rescue medication, as well as off-treatment data. Missing data for patients not providing any information at the visit were imputed based on the observed off-treatment data. In this multiple imputation analysis, 13.9% of the data were imputed for JARDIANCE 25 mg and 12.9% for glimepiride.

At Week 104, JARDIANCE 25 mg daily resulted in a statistically significant difference in change from baseline for body weight compared to glimepiride (-3.1 kg for JARDIANCE 25 mg vs. +1.3 kg for glimepiride; ANCOVA-LOCF, p-value <0.0001).

Add-On Combination Therapy with Pioglitazone with or without Metformin

A total of 498 patients with type 2 diabetes mellitus participated in a double-blind, placebo-controlled trial to evaluate the efficacy of JARDIANCE in combination with pioglitazone, with or without metformin.

Patients with inadequately controlled type 2 diabetes mellitus on metformin at a dose of at least 1,500 mg per day and pioglitazone at a dose of at least 30 mg per day were placed into an open-label placebo run-in for 2 weeks. Patients with inadequate glycemic control and an HbA1c between 7% and 10% after the run-in period were randomized to placebo, JARDIANCE 10 mg, or JARDIANCE 25 mg.

Treatment with JARDIANCE 10 mg or 25 mg daily resulted in statistically significant reductions in HbA1c (p-value <0.0001), FPG, and body weight compared with placebo (see Table 10).

Table 10Results of Placebo-Controlled Trial for JARDIANCE in Combination Therapy with Pioglitazone
 | JARDIANCE 10 mg N=165 | JARDIANCE 25 mg N=168 | Placebo N=165
HbA1c (%)a
Baseline (mean) | 8.1 | 8.1 | 8.2
Change from baseline (adjusted mean) | -0.6 | -0.7 | -0.1
Difference from placebo + pioglitazone (adjusted mean) (95% CI) | -0.5b (-0.7, -0.3) | -0.6b (-0.8, -0.4) | --
Patients [n (%)] achieving HbA1c <7% | 36 (24%) | 48 (30%) | 12 (8%)
FPG (mg/dL)c
Baseline (mean) | 152 | 152 | 152
Change from baseline (adjusted mean) | -17 | -22 | 7
Difference from placebo + pioglitazone (adjusted mean) (97.5% CI) | -23b (-31.8, -15.2) | -28b (-36.7, -20.2) | --
Body Weight
Baseline mean in kg | 78 | 79 | 78
% change from baseline (adjusted mean) | -2.0 | -1.8 | 0.6
Difference from placebo (adjusted mean) (95% CI) | -2.6b (-3.4, -1.8) | -2.4b (-3.2, -1.6) | --
aModified intent-to-treat population. Last observation on trial (LOCF) was used to impute missing data at Week 24. At Week 24, 10.9%, 8.3%, and 20.6% was imputed for patients randomized to JARDIANCE 10 mg, JARDIANCE 25 mg, and placebo, respectively.
bANCOVA p-value <0.0001 (HbA1c: ANCOVA model includes baseline HbA1c, treatment, renal function, and background medication. Body weight and FPG: same model used as for HbA1c but additionally including baseline body weight/baseline FPG, respectively.)
cFPG (mg/dL); for JARDIANCE 10 mg, n=163

Add-On Combination with Insulin with or without Metformin and/or Sulfonylureas

A total of 494 patients with type 2 diabetes mellitus inadequately controlled on insulin, or insulin in combination with oral drugs participated in a double-blind, placebo-controlled trial to evaluate the efficacy of JARDIANCE as add-on therapy to insulin over 78 weeks.

Patients entered a 2-week placebo run-in period on basal insulin (e.g., insulin glargine, insulin detemir, or NPH insulin) with or without metformin and/or sulfonylurea background therapy. Following the run-in period, patients with inadequate glycemic control were randomized to the addition of JARDIANCE 10 mg, JARDIANCE 25 mg, or placebo. Patients were maintained on a stable dose of insulin prior to enrollment, during the run-in period, and during the first 18 weeks of treatment. For the remaining 60 weeks, insulin could be adjusted. The mean total daily insulin dose at baseline for JARDIANCE 10 mg, 25 mg, and placebo was 45 IU, 48 IU, and 48 IU, respectively.

JARDIANCE used in combination with insulin (with or without metformin and/or sulfonylurea) provided statistically significant reductions in HbA1c and FPG compared to placebo after both 18 and 78 weeks of treatment (see Table 11). JARDIANCE 10 mg or 25 mg daily also resulted in statistically significantly greater percent body weight reduction compared to placebo.

Table 11Results at Week 18 and 78 for a Placebo-Controlled Trial for JARDIANCE in Combination with Insulin
 | 18 weeks (no insulin adjustment) |  |  | 78 weeks (adjustable insulin dose after 18 weeks)
 | JARDIANCE 10 mg N=169 | JARDIANCE 25 mg N=155 | Placebo N=170 | JARDIANCE 10 mg N=169 | JARDIANCE 25 mg N=155 | Placebo N=170
HbA1c (%)a
Baseline (mean) | 8.3 | 8.3 | 8.2 | 8.3 | 8.3 | 8.2
Change from baseline (adjusted mean) | -0.6 | -0.7 | 0 | -0.4 | -0.6 | 0.1
Difference from placebo (adjusted mean) (97.5% CI) | -0.6b (-0.8, -0.4) | -0.7b (-0.9, -0.5) | -- | -0.5b (-0.7, -0.3) | -0.7b (-0.9, -0.5) | --
Patients (%) achieving HbA1c <7% | 18.0 | 19.5 | 5.5 | 12.0 | 17.5 | 6.7
FPG (mg/dL)
Baseline (mean) | 138 | 146 | 142 | 138 | 146 | 142
Change from baseline (adjusted mean, SE) | -17.9 (3.2) | -19.1 (3.3) | 10.4 (3.1) | -10.1 (3.2) | -15.2 (3.4) | 2.8 (3.2)
Difference from placebo (adjusted mean) (95% CI) | -28.2b (-37.0, -19.5) | -29.5b (-38.4, -20.6) | -- | -12.9c (-21.9, 3.9) | -17.9b (-27.0, -8.8) | --
Body Weight
Baseline mean in kg | 92 | 95 | 90 | 92 | 95 | 90
% change from baseline (adjusted mean) | -1.8 | -1.4 | -0.1 | -2.4 | -2.4 | 0.7
Difference from placebo (adjusted mean) (95% CI) | -1.7d (-3.0, -0.5) | -1.3e (-2.5, -0.0) | -- | -3.0b (-4.4, -1.7) | -3.0b (-4.4, -1.6) | --
aModified intent-to-treat population. Last observation on trial (LOCF) was used to impute missing data at Week 18 and 78. At Week 18, 21.3%, 30.3%, and 21.8% was imputed for patients randomized to JARDIANCE 10 mg, JARDIANCE 25 mg, and placebo, respectively. At Week 78, 32.5%, 38.1% and 42.4% was imputed for patients randomized to JARDIANCE 10 mg, JARDIANCE 25 mg, and placebo, respectively.
bANCOVA p-value <0.0001 (HbA1c: ANCOVA model includes baseline HbA1c, treatment, and region; FPG: MMRM model includes baseline FPG, baseline HbA1c, treatment, region, visit and visit by treatment interaction. Body weight: MMRM model includes baseline body weight, baseline HbA1c, treatment, region, visit and visit by treatment interaction.
cp-value=0.0049
dp-value=0.0052
ep-value=0.0463

Add-on Combination with MDI Insulin with or without Metformin

A total of 563 patients with type 2 diabetes mellitus inadequately controlled on multiple daily injections (MDI) of insulin (total daily dose >60 IU), alone or in combination with metformin, participated in a double-blind, placebo-controlled trial to evaluate the efficacy of JARDIANCE as add-on therapy to MDI insulin over 18 weeks.

Patients entered a 2-week placebo run-in period on MDI insulin with or without metformin background therapy. Following the run-in period, patients with inadequate glycemic control were randomized to the addition of JARDIANCE 10 mg, JARDIANCE 25 mg, or placebo. Patients were maintained on a stable dose of insulin prior to enrollment, during the run-in period, and during the first 18 weeks of treatment. The mean total daily insulin dose at baseline for JARDIANCE 10 mg, JARDIANCE 25 mg, and placebo was 88.6 IU, 90.4 IU, and 89.9 IU, respectively.

JARDIANCE 10 mg or 25 mg daily used in combination with MDI insulin (with or without metformin) provided statistically significant reductions in HbA1c compared to placebo after 18 weeks of treatment (see Table 12).

Table 12Results at Week 18 for a Placebo-Controlled Trial for JARDIANCE in Combination with Insulin and with or without Metformin
 | JARDIANCE 10 mg N=186 | JARDIANCE 25 mg N=189 | Placebo N=188
HbA1c (%)a
Baseline (mean) | 8.4 | 8.3 | 8.3
Change from baseline (adjusted mean) | -0.9 | -1.0 | -0.5
Difference from placebo (adjusted mean) (95% CI) | -0.4b (-0.6, -0.3) | -0.5b (-0.7, -0.4) | --
aModified intent-to-treat population. Last observation on trial (LOCF) was used to impute missing data at Week 18. At Week 18, 23.7%, 22.8% and 23.4% was imputed for patients randomized to JARDIANCE 10 mg, JARDIANCE 25 mg, and placebo, respectively.
bANCOVA p-value <0.0001 (HbA1c: ANCOVA model includes baseline HbA1c, treatment, renal function, geographical region, and background medication).

During an extension period with treatment for up to 52 weeks, insulin could be adjusted to achieve defined glucose target levels. The change from baseline in HbA1c was maintained from 18 to 52 weeks with both JARDIANCE 10 mg and 25 mg. After 52 weeks, JARDIANCE 10 mg or 25 mg daily resulted in statistically greater percent body weight reduction compared to placebo (p-value <0.0001). The mean change in body weight from baseline was -1.95 kg for JARDIANCE 10 mg, and -2.04 kg for JARDIANCE 25 mg.

Renal Impairment

A total of 738 patients with type 2 diabetes mellitus and a baseline eGFR less than 90 mL/min/1.73 m^2 participated in a randomized, double-blind, placebo-controlled, parallel-group trial to evaluate the efficacy of JARDIANCE in patients with type 2 diabetes mellitus and renal impairment. The trial population comprised of 290 patients with mild renal impairment (eGFR 60 to less than 90 mL/min/1.73 m^2), 374 patients with moderate renal impairment (eGFR 30 to less than 60 mL/min/1.73 m^2), and 74 with severe renal impairment (eGFR less than 30 mL/min/1.73 m^2). A total of 194 patients with moderate renal impairment had a baseline eGFR of 30 to less than 45 mL/min/1.73 m^2 and 180 patients had a baseline eGFR of 45 to less than 60 mL/min/1.73 m^2.

At Week 24, JARDIANCE 25 mg provided statistically significant reduction in HbA1c relative to placebo in patients with mild to moderate renal impairment (see Table 13). A statistically significant reduction relative to placebo was also observed with JARDIANCE 25 mg in patients with either mild [-0.7 (95% CI: -0.9, -0.5)] or moderate [-0.4 (95% CI: -0.6, -0.3)] renal impairment and with JARDIANCE 10 mg in patients with mild [-0.5 (95% CI: -0.7, -0.3)] renal impairment.

The glucose lowering efficacy of JARDIANCE 25 mg decreased with decreasing level of renal function in the mild to moderate range. Least square mean HbA1c changes at 24 weeks were -0.6%, -0.5%, and -0.2% for those with a baseline eGFR of 60 to less than 90 mL/min/1.73 m^2, 45 to less than 60 mL/min/1.73 m^2, and 30 to less than 45 mL/min/1.73 m^2, respectively [see Dosage and Administration (2) and Use in Specific Populations (8.6)]. For placebo, least square mean HbA1c changes at 24 weeks were 0.1%, -0.1%, and 0.2% for patients with a baseline eGFR of 60 to less than 90 mL/min/1.73 m^2, 45 to less than 60 mL/min/1.73 m^2, and 30 to less than 45 mL/min/1.73 m^2, respectively.

Table 13Results at Week 24 (LOCF) of Placebo-Controlled Trial for JARDIANCE in Adults with Type 2 Diabetes Mellitus and Renal Impairment
 | Mild and Moderate Impairmentb
 | JARDIANCE 25 mg
HbA1c
Number of patients | n=284
Comparison vs placebo (adjusted mean) (95% CI) | -0.5a (-0.6, -0.4)
ap-value <0.0001 (HbA1c: ANCOVA model includes baseline HbA1c, treatment, renal function, and background medication)
beGFR 30 to less than 90 mL/min/1.73 m^2 - Modified intent-to-treat population. Last observation on trial (LOCF) was used to impute missing data at Week 24. At Week 24, 24.6% and 26.2% was imputed for patients randomized to JARDIANCE 25 mg and placebo, respectively.

For patients with severe renal impairment, the analyses of changes in HbA1c and FPG showed no discernible treatment effect of JARDIANCE 25 mg compared to placebo [see Indications and Usage (1), Dosage and Administration (2.1, 2.2) and Use in Specific Populations (8.6)].

14.2 Glycemic Control Trial in Pediatric Patients Aged 10 to 17 Years with Type 2 Diabetes Mellitus

DINAMO (NCT03429543) was a 26-week, double-blind, randomized, placebo-controlled, parallel group trial, with a double-blind active treatment safety extension period up to 52 weeks to assess the efficacy of JARDIANCE. The trial enrolled pediatric patients aged 10 to 17 years with inadequately controlled type 2 diabetes mellitus (HbA1c 6.5 to 10.5%). Patients treated with metformin (at least 1,000 mg daily or maximally tolerated dose), with or without insulin therapy, and those with a history of intolerance to metformin therapy were enrolled. Patients were randomized to 3 treatment arms (JARDIANCE 10 mg, a dipeptidyl peptidase-4 (DPP-4) inhibitor or placebo), over 26 weeks. Patients in the JARDIANCE 10 mg group who failed to achieve HbA1c <7.0% at Week 12 underwent a second randomization at Week 14 to remain on the 10 mg dose or increase to 25 mg. Patients on placebo were re-randomized at Week 26 to one of the JARDIANCE doses (10 mg or 25 mg) or a DPP-4 inhibitor.

A total of 157 patients were treated with either JARDIANCE (10 mg or 25 mg; N=52), a DPP-4 inhibitor (N=52), or placebo (N=53). Background therapies as adjunct to diet and exercise included metformin (51%), a combination of metformin and insulin (40.1%), insulin (3.2%), or none (5.7%). The mean HbA1c at baseline was 8.0% and the mean duration of type 2 diabetes mellitus was 2.1 years. The mean age was 14.5 years (range: 10-17 years) and 51.6% were aged 15 years and older. Approximately, 50% were White, 6% were Asian, 31% were Black or African American, and 38% were of Hispanic or Latino ethnicity. The mean BMI was 36.0 kg/m^2 and mean BMI Z-score was 3.0. Patients with an eGFR less than 60 mL/min/1.73 m^2 were not enrolled in the trial. Approximately 25% of the study population had microalbuminuria or macroalbuminuria.

At Week 26, treatment with JARDIANCE was superior in reducing HbA1c from baseline versus placebo (see Table 14).

Table 14Results at Week 26 for a Placebo-Controlled Trial for JARDIANCE in Combination with Metformin and/or Insulin or as Monotherapy in Pediatric Patients Aged 10 to 17 Years with Type 2 Diabetes Mellitusa
 | JARDIANCE 10 mg and 25 mg | Placebo
HbA1c (%)b
Number of patients | n=52 | n=53
Baseline (mean) | 8.0 | 8.1
Change from baselinec | -0.2 | 0.7
Difference from placeboc (95% CI) | -0.8e (-1.5, -0.2) | --
FPG (mg/dL)b,d
Number of patients | n=48 | n=52
Baseline (mean) | 154 | 159
Change from baselinec | -19 | 17
Difference from placeboc (95% CI) | -36 (-60.7, -10.7) | --
aModified intent-to-treat set (All randomized and treated patients with baseline measurement).
bMultiple imputations using placebo wash-out approach with 500 iterations for missing data. Imputed for HbA1c
(Jardiance N=5 (9.6 %), Placebo N=3 (5.7%)), for FPG (Jardiance N=4 (8.3%), Placebo N=2 (3.8%)).
cLeast-Square Mean from Analysis of Covariance (ANCOVA) adjusted for baseline value and baseline age stratum (< 15 years vs 15
to < 18 years).
dNot evaluated for statistical significance, not part of sequential testing procedure.
ep-value=0.0116 (two-sided)

14.3 Cardiovascular Outcomes in Adults with Type 2 Diabetes Mellitus and Atherosclerotic Cardiovascular Disease

The effect of JARDIANCE on cardiovascular (CV) risk in adult patients with type 2 diabetes mellitus and established, stable, atherosclerotic CV disease was evaluated in the EMPA-REG OUTCOME trial, a multicenter, multinational, randomized, double-blind parallel group trial. The trial compared the risk of experiencing a major adverse cardiovascular event (MACE) between JARDIANCE and placebo when these were added to and used concomitantly with standard of care treatments for diabetes mellitus and atherosclerotic CV disease. Concomitant antidiabetic medications were to be kept stable for the first 12 weeks of the trial. Thereafter, antidiabetic and atherosclerotic therapies could be adjusted, at the discretion of investigators, to ensure participants were treated according to the standard care for these diseases.

A total of 7,020 patients were treated (JARDIANCE 10 mg = 2,345; JARDIANCE 25 mg = 2,342; placebo = 2,333) and followed for a median of 3.1 years. Approximately 72% of the trial population was White, 22% was Asian, and 5% was Black. The mean age was 63 years and approximately 72% were male.

All patients in the trial had inadequately controlled type 2 diabetes mellitus at baseline (HbA1c greater than or equal to 7%). The mean HbA1c at baseline was 8.1% and 57% of participants had diabetes mellitus for more than 10 years. Approximately 31%, 22% and 20% reported a past history of neuropathy, retinopathy and nephropathy to investigators, respectively and the mean eGFR was 74 mL/min/1.73 m^2. At baseline, patients were treated with one (~30%) or more (~70%) antidiabetic medications including metformin (74%), insulin (48%), and sulfonylurea (43%).

All patients had established atherosclerotic CV disease at baseline including one (82%) or more (18%) of the following: a documented history of coronary artery disease (76%), stroke (23%) or peripheral artery disease (21%). At baseline, the mean systolic blood pressure was 136 mmHg, the mean diastolic blood pressure was 76 mmHg, the mean LDL was 86 mg/dL, the mean HDL was 44 mg/dL, and the mean urinary albumin to creatinine ratio (UACR) was 175 mg/g. At baseline, approximately 81% of patients were treated with renin angiotensin system inhibitors, 65% with beta-blockers, 43% with diuretics, 77% with statins, and 86% with antiplatelet agents (mostly aspirin).

The primary endpoint in EMPA-REG OUTCOME was the time to first occurrence of a Major Adverse Cardiac Event (MACE). A major adverse cardiac event was defined as occurrence of either a CV death or a non-fatal myocardial infarction (MI) or a non-fatal stroke. The statistical analysis plan had pre-specified that the 10 and 25 mg doses would be combined. A Cox proportional hazards model was used to test for non-inferiority against the pre-specified risk margin of 1.3 for the hazard ratio of MACE and superiority on MACE if non-inferiority was demonstrated. Type-1 error was controlled across multiples tests using a hierarchical testing strategy.

JARDIANCE significantly reduced the risk of first occurrence of primary composite endpoint of CV death, non-fatal myocardial infarction, or non-fatal stroke (HR: 0.86; 95% CI: 0.74, 0.99). The treatment effect was due to a significant reduction in the risk of CV death in subjects randomized to empagliflozin (HR: 0.62; 95% CI: 0.49, 0.77), with no change in the risk of non-fatal myocardial infarction or non-fatal stroke (see Table 15 and Figures 5 and 6). Results for the 10 mg and 25 mg empagliflozin dosages were consistent with results for the combined dosage groups.

Table 15Treatment Effect for the Primary Composite Endpoint and its Componentsa
 | Placebo N=2,333 | JARDIANCE N=4,687 | Hazard ratio vs placebo (95% CI)
Composite of CV death, non-fatal myocardial infarction, non-fatal stroke (time to first occurrence)b | 282 (12.1%) | 490 (10.5%) | 0.86 (0.74, 0.99)
Non-fatal myocardial infarctionc | 121 (5.2%) | 213 (4.5%) | 0.87 (0.70, 1.09)
Non-fatal strokec | 60 (2.6%) | 150 (3.2%) | 1.24 (0.92, 1.67)
CV deathc | 137 (5.9%) | 172 (3.7%) | 0.62 (0.49, 0.77)
aTreated set (patients who had received at least one dose of trial drug)
bp-value for superiority (2-sided) 0.04
cTotal number of events

Figure 5 Estimated Cumulative Incidence of First MACE

Figure 6 Estimated Cumulative Incidence of CV Death

The efficacy of JARDIANCE on CV death was generally consistent across major demographic and disease subgroups.

Vital status was obtained for 99.2% of subjects in the trial. A total of 463 deaths were recorded during the EMPA-REG OUTCOME trial. Most of these deaths were categorized as CV deaths. The non-CV deaths were only a small proportion of deaths and were balanced between the treatment groups (2.1% in patients treated with JARDIANCE, and 2.4% of patients treated with placebo).

14.4 Heart Failure Trials in Adults

EMPEROR-Reduced (NCT03057977) was a double-blind trial conducted in adults with chronic heart failure (New York Heart Association [NYHA] functional class II-IV) with left ventricular ejection fraction (LVEF) ≤40% to evaluate the efficacy of JARDIANCE as adjunct to standard of care heart failure therapy.

Of 3,730 patients, 1,863 were randomized to JARDIANCE 10 mg and 1,867 to placebo and were followed for a median of 16 months. The mean age of the trial population was 67 years (range: 25 to 94 years) and 76% were men, 24% were women, and 27% were 75 years of age or older. Approximately 71% of the trial population were White, 18% Asian, and 7% Black or African American. At baseline, 50% of the patients had type 2 diabetes mellitus.

At randomization, 75% of patients were NYHA class II, 24% were class III, and 0.5% were class IV. The mean LVEF was 28%. At baseline, the mean eGFR was 62 mL/min/1.73 m^2 and the median urinary albumin to creatinine ratio (UACR) was 22 mg/g. Approximately half of the patients (52%) had eGFR equal to or above 60 mL/min/1.73 m^2, 24% had eGFR 45 to less than 60 mL/min/1.73 m^2, 19% had eGFR 30 to less than 45 mL/min/1.73 m^2, and 5% had eGFR 20 to less than 30 mL/min/1.73 m^2.

At baseline, 88% of patients were treated with angiotensin-converting enzyme (ACE) inhibitors, angiotensin receptor blockers (ARB), or angiotensin receptor-neprilysin inhibitors (ARNI), 95% with beta-blockers, 71% with mineralocorticoid receptor antagonists (MRA), and 95% with diuretics.

The primary endpoint was the time to first event of either cardiovascular (CV) death or hospitalization for heart failure (HHF). First and recurrent HHF was assessed as a key secondary endpoint.

JARDIANCE was superior in reducing the risk of the primary composite endpoint of cardiovascular death or hospitalization for heart failure compared with placebo, mostly through a reduction in hospitalization for heart failure. JARDIANCE reduced the risk of first and recurrent HHF (see Table 16 and Figures 7 and 8).

Table 16Treatment Effect for the Primary Composite Endpoint, its Components, and Key Secondary Endpoints
 | Placebo N=1,867 | JARDIANCE 10 mg N=1,863 | Hazard ratio vs placebo (95% CI) | p-value
 | Number of Patients (%)
CV death or HHFa | 462 (24.7%) | 361 (19.4%) | 0.75 (0.65, 0.86) | <0.0001
CV deatha,b | 202 (10.8%) | 187 (10.0%) | 0.92 (0.75, 1.12)
HHFa | 342 (18.3%) | 246 (13.2%) | 0.69 (0.59, 0.81)
 | Number of Events
First and recurrent HHFc | 553 | 388 | 0.70 (0.58, 0.85) | 0.0003
aTime to first event
bIncludes deaths following hospitalization
cJoint frailty model accounting for CV death

Figure 7 Time to First Occurrence of the Primary Composite Endpoint of CV Death or Hospitalization for Heart Failure

Figure 8 Time to Event of Hospitalization for Heart Failure (First and Recurrent)

The results of the primary composite were generally consistent across the pre-specified subgroups (see Figure 9).

Figure 9 Treatment Effects for the Primary Composite Endpoint (CV Death and Hospitalization for Heart Failure) Subgroup Analysis (EMPEROR-Reduced)

LVEF >30%: Includes both above and below the median NT-proBNP. To be eligible for inclusion, patients with an LVEF >30% were required to meet a higher NT-proBNP threshold than those with LVEF ≤30%, unless they additionally had a history of HHF within the past 12 months.

EMPEROR-Preserved (NCT03057951) was a double-blind trial conducted in adults with chronic heart failure NYHA Class II-IV with LVEF >40% to evaluate the efficacy of JARDIANCE as adjunct to standard of care therapy.

Of 5,988 patients, 2,997 were randomized to JARDIANCE 10 mg and 2,991 to placebo and were followed for a median of 26 months. The mean age of the trial population was 72 years (range: 22 to 100 years) and 55% were men, 45% were women, and 43% were 75 years of age or older. Approximately 76% of the trial population were White, 14% Asian, and 4% Black or African American.

At randomization, 82% of patients were NYHA class II, 18% were class III, and 0.3% were class IV. The EMPEROR-Preserved trial population included patients with a LVEF <50% (33.1%), with a LVEF 50 to <60% (34.4%) and a LVEF ≥60% (32.5%). At baseline, the mean eGFR was 61 mL/min/1.73 m^2 and the median urinary albumin to creatinine ratio (UACR) was 21 mg/g. Approximately half of the patients (50%) had eGFR equal to or above 60 mL/min/1.73 m^2, 26% had eGFR 45 to less than 60 mL/min/1.73 m^2, 19% had eGFR 30 to less than 45 mL/min/1.73 m^2, and 5% had eGFR 20 to less than 30 mL/min/1.73 m^2.

At baseline, 81% of patients were treated with ACE inhibitors, ARBs, or ARNI, 86% with beta-blockers, 38% with MRAs, and 86% with diuretics.

The primary endpoint was the time to first event of either CV death or HHF. First and recurrent HHF was assessed as a key secondary endpoint.

JARDIANCE was superior in reducing the risk of the primary composite endpoint compared with placebo, mostly through a reduction in hospitalization for heart failure. JARDIANCE reduced the risk of first and recurrent HHF (see Table 17 and Figures 10 and 11).

Table 17Treatment Effect for the Primary Composite Endpoint, its Components, and Key Secondary Endpoints
 | Placebo N=2,991 | JARDIANCE 10 mg N=2,997 | Hazard ratio vs placebo (95% CI) | p-value
 | Number of Patients (%)
CV death or HHFa | 511 (17.1%) | 415 (13.8%) | 0.79 (0.69, 0.90) | 0.0003
CV deatha,b | 244 (8.2%) | 219 (7.3%) | 0.91 (0.76, 1.09)
HHFa | 352 (11.8%) | 259 (8.6%) | 0.71 (0.60, 0.83)
 | Number of Events
First and recurrent HHFc | 541 | 407 | 0.73 (0.61, 0.88) | 0.0009
aTime to first event
bIncludes deaths following hospitalization
cJoint frailty model accounting for CV death

Figure 10 Time to First Occurrence of the Primary Composite Endpoint of CV Death or Hospitalization for Heart Failure

Figure 11 Time to Event of Hospitalization for Heart Failure (First and Recurrent)

The results of the primary composite endpoint were consistent across the pre-specified subgroups (see Figure 12).

Figure 12 Treatment Effects for the Primary Composite Endpoint (CV Death or Hospitalization for Heart Failure) Subgroup Analysis (EMPEROR-Preserved)

14.5 Chronic Kidney Disease Trial in Adults

EMPA-KIDNEY (NCT03594110) was a randomized, double-blind, placebo-controlled trial conducted in adults with chronic kidney disease (eGFR ≥20 to <45 mL/min/1.73 m^2; or eGFR ≥45 to <90 mL/min/1.73 m^2 with urine albumin to creatinine ratio [UACR] ≥200 mg/g). The trial excluded patients with polycystic kidney disease or patients requiring intravenous immunosuppressive therapy in the preceding three months or >45 mg of prednisone (or equivalent) at the time of screening. The primary objective of the trial was to assess the effects of empagliflozin as an adjunct to standard of care therapy, including RAS-inhibitor therapy when appropriate, on time to kidney disease progression or cardiovascular death.

A total of 6,609 patients, were equally randomized to JARDIANCE 10 mg or placebo and were followed for a median of 24 months.

The mean age of the study population was 63 years (range: 18 to 94 years) and 67% were male. Approximately 58% of the study population were White, 36% Asian, and 4% Black or African American. Approximately 44% of the patients had type 2 diabetes mellitus.

At baseline, the mean eGFR was 37 mL/min/1.73 m^2, 21% of patients had an eGFR equal to or above 45 mL/min/1.73 m^2, 44% had an eGFR 30 to less than 45 mL/min/1.73 m^2, and 35% had an eGFR less than 30 mL/min/1.73 m^2. The median UACR was 329 mg/g, 20% of patients had a UACR <30 mg/g, 28% had a UACR 30 to ≤300mg/g, and 52% had a UACR >300 mg/g. Approximately 1% of patients had type 1 diabetes at baseline. The most common etiologies of CKD were diabetic nephropathy/diabetic kidney disease (31%), glomerular disease (25%), hypertensive/renovascular disease (22%) and other/unknown (22%).

At baseline, 85% of patients were treated with ACE inhibitor or ARB, 64% with statins, and 34% with antiplatelet agents.

JARDIANCE was superior to placebo in reducing the risk of the primary composite endpoint of sustained ≥40% eGFR decline, sustained eGFR <10 mL/min/1.73 m^2, progression to end-stage kidney disease, or CV or renal death. The treatment effect reflected a reduction in a sustained ≥40% eGFR decline, sustained eGFR <10 mL/min/1.73 m^2, progression to end-stage kidney disease, and CV death. There were few renal deaths during the trial. JARDIANCE also reduced the risk of first and recurrent hospitalization (see Table 18 and Figure 13); information collected on the reason for hospitalization was insufficient to further characterize the benefit.

Table 18Treatment Effect for the Primary Composite Endpoint, its Components and Key Secondary Endpoints
 | Placebo N=3,305 | JARDIANCE 10 mg N=3,304 | Hazard ratio vs placebo (95% CI) | p-value
 | Number of Patients (%)
Composite of sustained ≥40% eGFR decline, sustained eGFR <10 mL/min/1.73 m^2, ESKDa, or CV or renal death (time to first occurrence) | 558 (16.9) | 432 (13.1) | 0.72 (0.64, 0.82) | <0.0001
Sustained ≥40% eGFR decline | 474 (14.3) | 359 (10.9) | 0.70 (0.61, 0.81)
ESKDa or sustained eGFR <10 mL/min/1.73 m^2 | 221 (6.7) | 157 (4.8) | 0.69 (0.56, 0.84)
Renal deathb | 4 (0.1) | 4 (0.1)
CV death | 69 (2.1) | 59 (1.8) | 0.84 (0.60, 1.19)
 | Number of Events
First and recurrent hospitalization c | 1,895 | 1,611 | 0.86 (0.78, 0.95) | 0.0025
CV=Cardiovascular, eGFR=Estimated glomerular filtration rate, ESKD=End-stage kidney disease
aESKD is defined as the initiation of maintenance dialysis or receipt of a kidney transplant.
bThere were too few events of renal death to compute a reliable hazard ratio.
cInformation collected on the reason for hospitalization was insufficient to further characterize the benefit.

Figure 13 Time to First Occurrence of the Primary Composite Endpoint, Sustained ≥40% eGFR Decline, Sustained eGFR <10 mL/min/1.73 m^2, ESKD or Renal Death, or CV Death

The results of the primary composite endpoint were generally consistent across the pre-specified subgroups examined, including eGFR categories, underlying cause of kidney disease, diabetes status, or background use of RAS inhibitors (see Figure 14). The treatment benefit with JARDIANCE on the primary composite endpoint was not evident in patients with very low levels of albuminuria, however there were few events in these patients.

Figure 14 Treatment Effects for the Primary Composite Endpoint (Sustained ≥40% eGFR Decline, Sustained eGFR <10 mL/min/1.73 m^2, ESKD or Renal Death, or CV Death) Subgroup Analysis (EMPA-KIDNEY)

*=Trend test

16 HOW SUPPLIED/STORAGE AND HANDLING

JARDIANCE tablets are available as follows:

10 mg tablets: pale yellow, round, biconvex, and bevel-edged film-coated tablets debossed with "S 10" on one side and the Boehringer Ingelheim company symbol on the other side.
Bottles of approximately 720 film-coated tablets, NDC 55154-0411-8

25 mg tablets: pale yellow, oval, biconvex film-coated tablets, debossed with "S 25" on one side and the Boehringer Ingelheim company symbol on the other side.
Bottles of approximately 990 film-coated tablets, NDC 55154-0412-8

Dispense in a well-closed container as defined in the USP.

Storage

Store at 20°C to 25°C (68°F to 77°F); excursions permitted to 15°C to 30°C (59°F to 86°F) [see USP Controlled Room Temperature].

17 PATIENT COUNSELING INFORMATION

Advise the patient to read the FDA-approved patient labeling (Medication Guide).

Diabetic Ketoacidosis in Patients with Type 1 Diabetes Mellitus and Other Ketoacidosis

In patients with type 1 diabetes mellitus, inform them that using JARDIANCE can increase their risk of life-threatening diabetic ketoacidosis and that fatal ketoacidosis has occurred. For all other patients, inform them that JARDIANCE can cause potentially fatal ketoacidosis and that type 2 diabetes mellitus and pancreatic disorders (e.g., history of pancreatitis or pancreatic surgery) are risk factors.

Educate all patients on precipitating factors (such as insulin dose reduction or missed insulin doses, infection, reduced caloric intake, ketogenic diet, surgery, dehydration, and alcohol abuse) and symptoms of ketoacidosis (including nausea, vomiting, abdominal pain, tiredness, and labored breathing). Inform patients that blood glucose may be normal even in the presence of ketoacidosis.

Advise patients that they may be asked to monitor ketones. If symptoms of ketoacidosis occur, instruct patients to discontinue JARDIANCE and seek medical attention immediately [see Warnings and Precautions (5.1)].

Volume Depletion

Inform patients that symptomatic hypotension may occur with JARDIANCE and advise them to contact their healthcare provider if they experience such symptoms [see Warnings and Precautions (5.2)]. Inform patients that dehydration may increase the risk for hypotension, and to maintain adequate fluid intake.

Genitourinary Infections, including Urosepsis, Pyelonephritis, Necrotizing Fasciitis of the Perineum (Fournier's Gangrene), and Genital Mycotic Infections

Counsel patients that genitourinary infections may occur when taking JARDIANCE and may become serious. Educate them on the symptoms and advise them to seek medical advice if symptoms occur. Specifically, advise patients to promptly seek medical attention if they develop pain or tenderness, redness, or swelling of the genitals or the area from the genitals back to the rectum, along with a fever above 100.4°F or malaise [see Warnings and Precautions (5.3)].

Hypoglycemia

Inform patients that hypoglycemia has been reported when JARDIANCE is used with insulin secretagogues or insulin. Hypoglycemia may occur in pediatric patients regardless of concomitant antidiabetic treatment. Educate patients or caregivers on the signs and symptoms of hypoglycemia [see Warnings and Precautions (5.4)].

Lower Limb Amputation

Counsel patients about the importance of routine preventative foot care. Instruct patients to monitor for new pain or tenderness, sores or ulcers, or infections involving the leg or foot and to seek medical advice immediately if such signs or symptoms develop [see Warnings and Precautions (5.5)].

Hypersensitivity Reactions

Inform patients that serious hypersensitivity reactions, such as urticaria and angioedema, have been reported with JARDIANCE. Advise patients to report immediately any skin reaction or angioedema, and to discontinue drug until they have consulted prescribing healthcare provider [see Warnings and Precautions (5.6)].

Laboratory Tests

Inform patients that elevated glucose in urinalysis is expected when taking JARDIANCE [see Drug Interactions (7)].

Pregnancy

Advise pregnant patients, and patients of reproductive potential, of the potential risk to a fetus with treatment with JARDIANCE [see Use in Specific Populations (8.1)]. Instruct patients to report pregnancies to their healthcare provider as soon as possible.

Lactation

Advise patients that breastfeeding is not recommended during treatment with JARDIANCE [see Use in Specific Populations (8.2)].

Missed Dose

Instruct patients to take JARDIANCE only as prescribed. If a dose is missed, it should be taken as soon as the patient remembers. Advise patients not to double their next dose [see Dosage and Administration (2.4)].

Distributed by:
Boehringer Ingelheim Pharmaceuticals, Inc.
Ridgefield, CT 06877 USA

Licensed from:
Boehringer Ingelheim International GmbH, Ingelheim, Germany

JARDIANCE is a registered trademark of and used under license from Boehringer Ingelheim International GmbH.

Boehringer Ingelheim Pharmaceuticals, Inc. either owns or uses the EMPA-REG OUTCOME®, EMPEROR-Reduced®, EMPEROR-Preserved®, and EMPA-KIDNEY® trademarks under license.

The other brands listed are trademarks of their respective owners and are not trademarks of Boehringer Ingelheim Pharmaceuticals, Inc.

Copyright © 2026 Boehringer Ingelheim International GmbH
ALL RIGHTS RESERVED

Distributed By:

Cardinal Health

Dublin, OH 43017

ER7381I Rev. C

ER7383 Rev. B

COL8914QA062026

SPL14754C

MEDICATION GUIDE
JARDIANCE® (jar DEE ans)
(empagliflozin tablets)
for oral use

What is the most important information I should know about JARDIANCE?
JARDIANCE can cause serious side effects, including:

- Diabetic ketoacidosis (increased ketones in your blood or urine) in people with type 1 and other ketoacidosis. JARDIANCE can cause ketoacidosis that can be life-threatening and may lead to death. Ketoacidosis is a serious condition which needs to be treated in a hospital. People with type 1 diabetes have a high risk of getting ketoacidosis. People with type 2 diabetes or pancreas problems also have an increased risk of getting ketoacidosis. Ketoacidosis can also happen in people who: are sick, cannot eat or drink as usual, skip meals, are on a diet high in fat and low in carbohydrates (ketogenic diet), take less than the usual amount of insulin or miss insulin doses, drink too much alcohol, have a loss of too much fluid from the body (volume depletion), or who have surgery. Ketoacidosis can happen even if your blood sugar is less than 250 mg/dL. Your healthcare provider may ask you to periodically check ketones in your urine or blood.
  Stop taking JARDIANCE and call your healthcare provider or get medical help right away if you get any of the following. If possible, check for ketones in your urine or blood, even if your blood sugar is less than 250 mg/dL:

- nausea
- vomiting
- stomach-area (abdominal) pain

- tiredness
- trouble breathing
- ketones in your urine or blood

- Dehydration. JARDIANCE can cause some people to become dehydrated (the loss of body water and salt). Dehydration may cause you to feel dizzy, faint, light-headed, or weak, especially when you stand up (orthostatic hypotension). There have been reports of sudden worsening of kidney function in people who are taking JARDIANCE. You may be at higher risk of dehydration if you:
  - take medicines to lower your blood pressure, including diuretics (water pills)
  - are on low sodium (salt) diet
  - have kidney problems
  - are 65 years of age or older
    Talk to your healthcare provider about what you can do to prevent dehydration including how much fluid you should drink on a daily basis. Call your healthcare provider right away if you reduce the amount of food or liquid you drink, for example if you are sick or you cannot eat, or start to lose liquids from your body, for example from vomiting, diarrhea or being in the sun too long.

What is JARDIANCE?
JARDIANCE is a prescription medicine used to:

- reduce the risk of cardiovascular death and hospitalization for heart failure in adults with heart failure, when the heart cannot pump enough blood to the rest of your body.
- reduce the risk of further worsening of kidney disease, end-stage kidney disease (ESKD), death due to cardiovascular disease, and hospitalization in adults with chronic kidney disease.
- reduce the risk of cardiovascular death in adults with type 2 diabetes and who also have known cardiovascular disease.
- lower blood sugar (glucose) along with diet and exercise in adults and children who are 10 years of age and older with type 2 diabetes.

JARDIANCE is not for use to lower blood sugar (glucose) in people with type 1 diabetes. It may increase their risk of diabetic ketoacidosis (increased ketones in blood or urine).
JARDIANCE is not for use to lower blood sugar (glucose) in people with type 2 diabetes who have severe kidney problems, because it may not work.
JARDIANCE is not for people with polycystic kidney disease, or who are taking or have recently received certain types of immunosuppressive therapy to treat kidney disease. JARDIANCE is not expected to work if you have these conditions.
It is not known if JARDIANCE is safe and effective in children under 10 years of age.

Who should not take JARDIANCE?
Do not take JARDIANCE if you:

- are allergic to empagliflozin or any of the ingredients in JARDIANCE. See the end of this Medication Guide for a complete list of ingredients in JARDIANCE. Symptoms of a serious allergic reaction to JARDIANCE may include:
  - rash
  - raised, red areas on your skin (hives)
  - swelling of your face, lips, mouth, and throat that may cause difficulty in breathing or swallowing
    If you have any of these symptoms, stop taking JARDIANCE and call your healthcare provider right away or go to the nearest hospital emergency room.

What should I tell my healthcare provider before taking JARDIANCE?
Before taking JARDIANCE, tell your healthcare provider about all of your medical conditions, including if you:

- have type 1 diabetes or have had diabetic ketoacidosis.
- have a decrease in your insulin dose.
- have a serious infection.
- have a history of infection of the vagina or penis.
- have a history of amputation.
- have kidney problems.
- have liver problems.
- have a history of urinary tract infections or problems with urination.
- are on a low sodium (salt) diet. Your healthcare provider may change your diet or your dose.
- are going to have surgery. Your healthcare provider may stop your JARDIANCE before you have surgery. Talk to your healthcare provider if you are having surgery about when to stop taking JARDIANCE and when to start it again.
- are eating less, or there is a change in your diet.
- are dehydrated.
- have or have had problems with your pancreas, including pancreatitis or surgery on your pancreas.
- drink alcohol very often or drink a lot of alcohol in the short term ("binge" drinking).
- have ever had an allergic reaction to JARDIANCE.
- are pregnant or plan to become pregnant. JARDIANCE may harm your unborn baby. If you become pregnant while taking JARDIANCE, tell your healthcare provider as soon as possible. Talk with your healthcare provider about the best way to control your blood sugar while you are pregnant.
- are breastfeeding or plan to breastfeed. JARDIANCE may pass into your breast milk and may harm your baby. Talk with your healthcare provider about the best way to feed your baby if you are taking JARDIANCE. Do not breastfeed while taking JARDIANCE.

Tell your healthcare provider about all the medicines you take, including prescription and over-the-counter medicines, vitamins, and herbal supplements.
JARDIANCE may affect the way other medicines work, and other medicines may affect how JARDIANCE works.
Know the medicines you take. Keep a list of them to show your healthcare provider and pharmacist when you get a new medicine.

How should I take JARDIANCE?

- Take JARDIANCE exactly as your healthcare provider tells you to take it.
- Take JARDIANCE by mouth 1 time in the morning each day, with or without food.
- Your healthcare provider will tell you how much JARDIANCE to take and when to take it. Your healthcare provider may change your dose if needed.
- Your healthcare provider may tell you to take JARDIANCE along with other diabetes medicines. Low blood sugar can happen more often when JARDIANCE is taken with certain other diabetes medicines. See "What are the possible side effects of JARDIANCE?"
- If you miss a dose, take it as soon as you remember. If it is almost time for your next dose, skip the missed dose and take the medicine at the next regularly scheduled time. Do not take two doses of JARDIANCE at the same time. Talk with your healthcare provider if you have questions about a missed dose.
- If you take too much JARDIANCE, call your healthcare provider or Poison Help line at 1-800-222-1222, or go to the nearest hospital emergency room right away.
- When taking JARDIANCE, you may have sugar in your urine, which will show up on a urine test.
- When your body is under some types of stress, such as fever, trauma (such as a car accident), infection, or surgery, the amount of diabetes medicine you need may change. Tell your healthcare provider right away if you have any of these conditions and follow your healthcare provider's instructions.
- Your healthcare provider may do certain blood tests before you start JARDIANCE and during treatment as needed.

What are the possible side effects of JARDIANCE?
JARDIANCE may cause serious side effects, including:

- See "What is the most important information I should know about JARDIANCE?"
- Genital and urinary tract infections. JARDIANCE can cause serious infections in your genital area or urinary tract that could require hospitalization. A rare but serious bacterial infection called necrotizing fasciitis can cause damage to the tissue under the skin in the area between and around the anus and genitals (perineum). This infection may require hospitalization, multiple surgeries, and could lead to death. Seek medical attention immediately if you have a fever or you are feeling very weak, tired or uncomfortable (malaise), and you develop any of the following symptoms in the area between and around your anus and genitals:

- pain or tenderness

- swelling

- redness of skin (erythema)

Also tell your healthcare provider if you have any of these signs or symptoms of urinary tract infections or yeast infections:

- Urinary tract infection:You may also have a fever, back pain, nausea, or vomiting.
  - burning feeling when you urinate
  - need to urinate often or right away
  - pain in the lower part of your stomach (pelvis)
  - blood in your urine
- Vaginal yeast infection:
  - vaginal odor
  - white or yellowish vaginal discharge (may be lumpy or look like cottage cheese)
  - vaginal itching
- Yeast infection of the skin around the penis (balanitis or balanoposthitis): If you are uncircumcised, swelling may make it difficult to pull back the skin around the tip of your penis. Other symptoms include:

- redness, itching, or swelling of the penis
- bad smelling discharge from the penis

- rash on the penis
- pain in the skin around the penis

Talk to your healthcare provider about what to do if you get symptoms of a yeast infection. They may suggest you use an over-the-counter antifungal medicine. Contact your healthcare provider right away if your symptoms do not improve after using an over-the-counter antifungal medicine.

- Low blood sugar (hypoglycemia). In adults, if you take JARDIANCE with another medicine that can cause low blood sugar, such as a sulfonylurea or insulin, your risk of getting low blood sugar is higher. In children 10 years of age and older, the risk for low blood sugar is higher with JARDIANCE even if you do not use another medicine that can also lower blood sugar. The dose of your sulfonylurea medicine or insulin may need to be lowered while you take JARDIANCE.
  Signs and symptoms of low blood sugar may include:

- headache
- drowsiness
- weakness

- irritability
- hunger
- fast heartbeat

- confusion
- shaking or feeling jittery

- dizziness
- sweating

- Amputations. SGLT2 inhibitors may increase your risk of lower limb amputations.
  You may be at a higher risk of lower limb amputation if you:
  - have a history of amputation
  - have had blocked or narrowed blood vessels, usually in your leg
  - have had diabetic foot infection, ulcers or sores
    Call your healthcare provider right away if you have new pain or tenderness, any sores, ulcers, or infections in your leg or foot. Talk to your healthcare provider about proper foot care.
- Serious allergic reactions. If you have any symptoms of a serious allergic reaction, stop taking JARDIANCE and call your healthcare provider right away or go to the nearest hospital emergency room. See "Who should not take JARDIANCE?".

The most common side effects of JARDIANCE include:

- urinary tract infections
- yeast infections in females

These are not all the possible side effects of JARDIANCE. For more information, ask your healthcare provider or pharmacist.
Call your doctor for medical advice about side effects. You may report side effects to FDA at 1-800-FDA-1088.

How should I store JARDIANCE?

- Store JARDIANCE at room temperature between 68°F to 77°F (20°C to 25°C).
- Keep JARDIANCE and all medicines out of the reach of children.

General information about the safe and effective use of JARDIANCE.
Medicines are sometimes prescribed for purposes other than those listed in a Medication Guide. Do not use JARDIANCE for a condition for which it is not prescribed. Do not give JARDIANCE to other people, even if they have the same symptoms you have. It may harm them.
You can ask your pharmacist or healthcare provider for information about JARDIANCE that is written for health professionals.

What are the ingredients in JARDIANCE?
Active Ingredient: empagliflozin
Inactive Ingredients: colloidal silicon dioxide, croscarmellose sodium, hydroxypropyl cellulose, lactose monohydrate, magnesium stearate, and microcrystalline cellulose. In addition, the film coating contains the following inactive ingredients: ferric oxide yellow, hypromellose, polyethylene glycol, talc, and titanium dioxide.
Distributed by: Boehringer Ingelheim Pharmaceuticals, Inc., Ridgefield, CT 06877 USA
Licensed from: Boehringer Ingelheim International GmbH, Ingelheim, Germany
JARDIANCE is a registered trademark of and used under license from Boehringer Ingelheim International GmbH.
Boehringer Ingelheim Pharmaceuticals, Inc. either owns or uses the EMPA-REG OUTCOME®, EMPEROR-Reduced®, EMPEROR-Preserved®, and EMPA-KIDNEY® trademarks under license.
The other brands listed are trademarks of their respective owners and are not trademarks of Boehringer Ingelheim Pharmaceuticals, Inc.
Copyright © 2026 Boehringer Ingelheim International GmbH
ALL RIGHTS RESERVED

Distributed By:

Cardinal Health

Dublin, OH 43017

ER7381I Rev. C

ER7383 Rev. B

COL8914QA062026
For more information about JARDIANCE, including current prescribing information and Medication Guide, go to www.jardiance.com, scan the code, or call Boehringer Ingelheim Pharmaceuticals, Inc. at 1-800-542-6257.

This Medication Guide has been approved by the U.S. Food and Drug Administration.

Revised: January 2026

Package/Label Display Panel

Contains Approximately

720 Tablets

JARDIANCE®

(empagliflozin) tablets

10 mg

Rx Only

WARNING: Keep out of reach of

children.

Package/Label Display Panel

Contains Approximately

990 Tablets

JARDIANCE®

(empagliflozin) tablets

25 mg

Rx Only

WARNING: Keep out of reach of

children.